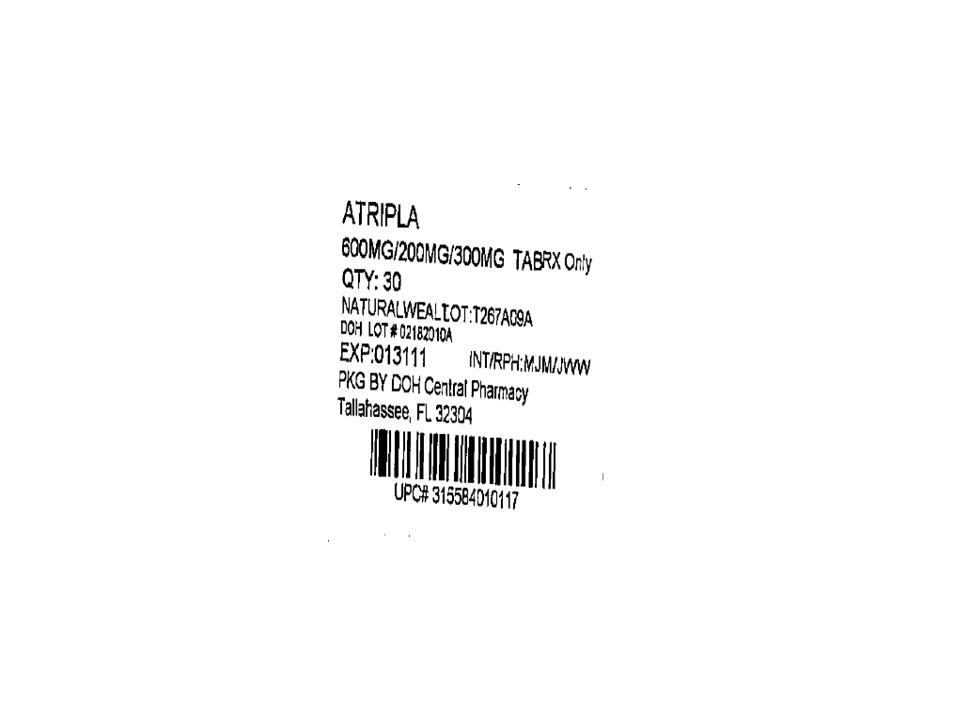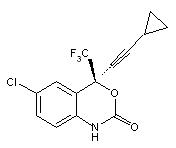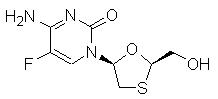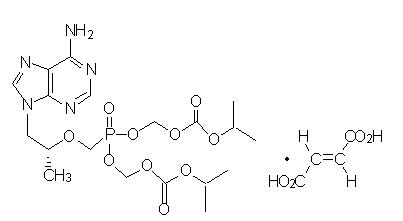 DRUG LABEL: Atripla
NDC: 53808-0208 | Form: TABLET, FILM COATED
Manufacturer: DOH CENTRAL PHARMACY
Category: prescription | Type: HUMAN PRESCRIPTION DRUG LABEL
Date: 20170123

ACTIVE INGREDIENTS: EFAVIRENZ 600 mg/1 1; EMTRICITABINE 200 mg/1 1; TENOFOVIR DISOPROXIL FUMARATE 300 mg/1 1
INACTIVE INGREDIENTS: CROSCARMELLOSE SODIUM; HYDROXYPROPYL CELLULOSE (TYPE H); MAGNESIUM STEARATE; CELLULOSE, MICROCRYSTALLINE; SODIUM LAURYL SULFATE; FERROSOFERRIC OXIDE; POLYETHYLENE GLYCOL, UNSPECIFIED; POLYVINYL ALCOHOL, UNSPECIFIED; FERRIC OXIDE RED; TALC; TITANIUM DIOXIDE

HIGHLIGHTS OF PRESCRIBING INFORMATION

These highlights do not include all the information needed to use ATRIPLA safely and effectively. See full prescribing information for ATRIPLA.
ATRIPLA® (efavirenz/emtricitabine/tenofovir disoproxil fumarate) tablets
Initial U.S. Approval: 2006

WARNINGS: LACTIC ACIDOSIS/SEVERE HEPATOMEGALY WITH STEATOSIS and POST TREATMENT EXACERBATION OF HEPATITIS B

See full prescribing information for complete boxed warning.

- Lactic acidosis and severe hepatomegaly with steatosis, including fatal cases, have been reported with the use of nucleoside analogs, including tenofovir disoproxil fumarate, a component of ATRIPLA. (5.1)
- ATRIPLA is not approved for the treatment of chronic hepatitis B virus (HBV) infection. Severe acute exacerbations of hepatitis B have been reported in patients coinfected with HBV and HIV-1 who have discontinued EMTRIVA or VIREAD, two of the components of ATRIPLA. Hepatic function should be monitored closely in these patients. If appropriate, initiation of anti-hepatitis B therapy may be warranted. (5.2)

RECENT MAJOR CHANGES

Boxed Warning | 1/2010
Warnings and Precautions
Patients Coinfected with HIV-1 and HBV (5.2) | 1/2010
New Onset or Worsening Renal Impairment (5.7) | 1/2010
Reproductive Risk Potential (5.8) | 1/2010
Decrease in Bone Mineral Density (5.11) | 1/2010

1 INDICATIONS AND USAGE

ATRIPLA, a combination of 2 nucleoside analog HIV-1 reverse transcriptase inhibitors and 1 non-nucleoside HIV-1 reverse transcriptase inhibitor, is indicated for use alone as a complete regimen or in combination with other antiretroviral agents for the treatment of HIV-1 infection in adults. (1)

DOSAGE AND ADMINISTRATION

- Recommended dose: One tablet once daily taken orally on an empty stomach, preferably at bedtime. (2)
- Dose in renal impairment: Should not be administered in patients with creatinine clearance <50 mL/min. (2)

3 DOSAGE FORMS AND STRENGTHS

Tablet containing 600 mg of efavirenz, 200 mg of emtricitabine and 300 mg of tenofovir disoproxil fumarate. (3)

CONTRAINDICATIONS

- Previously demonstrated hypersensitivity (e.g., Stevens-Johnson syndrome, erythema multiforme, or toxic skin eruptions) to efavirenz, a component of ATRIPLA. (4.1)
- For some drugs, competition for CYP3A by efavirenz could result in inhibition of their metabolism and create the potential for serious and/or life-threatening adverse reactions (e.g., cardiac arrhythmias, prolonged sedation, or respiratory depression). (4.2)

WARNINGS AND PRECAUTIONS

- Serious psychiatric symptoms: Immediate medical evaluation is recommended. (5.5, 6.1)
- Nervous system symptoms (NSS): NSS are frequent, usually begin 1–2 days after initiating therapy and resolve in 2–4 weeks. Dosing at bedtime may improve tolerability. NSS are not predictive of onset of psychiatric symptoms. (2, 5.6)
- New onset or worsening renal impairment: Can include acute renal failure and Fanconi syndrome. Assess creatinine clearance (CrCl) before initiating treatment with ATRIPLA. Monitor CrCl and serum phosphorus in patients at risk. Avoid administering ATRIPLA with concurrent or recent use of nephrotoxic drugs. (5.7)
- Pregnancy: Fetal harm can occur when administered to a pregnant woman during the first trimester. Women should be apprised of the potential harm to the fetus. (5.8)
- Rash: Discontinue if severe rash develops. (5.9, 6.1)
- Hepatotoxicity: Monitor liver function tests before and during treatment in patients with underlying hepatic disease, including hepatitis B and C, or marked transaminase elevations. (5.10, 8.6)
- Decreases in bone mineral density (BMD): Consider monitoring BMD in patients with a history of pathological fracture or who are at risk for osteopenia. (5.11)
- Convulsions: Use caution in patients with a history of seizures. (5.12)
- Immune reconstitution syndrome: May necessitate further evaluation and treatment. (5.13)
- Redistribution/accumulation of body fat: Observed in patients receiving antiretroviral therapy. (5.14)
- Coadministration with other products: Do not use with drugs containing efavirenz, emtricitabine or tenofovir disoproxil fumarate including SUSTIVA, TRUVADA, EMTRIVA, VIREAD; or with drugs containing lamivudine. Do not administer in combination with HEPSERA. (5.4)

ADVERSE REACTIONS

Most common adverse reactions (incidence ≥10%) observed in an active-controlled clinical study of efavirenz, emtricitabine, and tenofovir DF are diarrhea, nausea, fatigue, headache, dizziness, depression, insomnia, abnormal dreams, and rash. (6)

To report SUSPECTED ADVERSE REACTIONS, contact Gilead Sciences, Inc. at 1-800-GILEAD-5 or FDA at 1-800-FDA-1088 or www.fda.gov/medwatch

7 DRUG INTERACTIONS

- Efavirenz: Coadministration of efavirenz can alter the concentrations of other drugs and other drugs may alter the concentrations of efavirenz. The potential for drug-drug interactions must be considered before and during therapy. (4.2, 7.1, 12.3)
- Didanosine: Tenofovir disoproxil fumarate increases didanosine concentrations. Use with caution and monitor for evidence of didanosine toxicity (e.g., pancreatitis, neuropathy) when coadministered. Consider dose reductions or discontinuations of didanosine if warranted. (7.2)
- Atazanavir: Coadministration of ATRIPLA and atazanavir or atazanavir/ritonavir is not recommended. (7.3)
- Lopinavir/ritonavir: Coadministration increases tenofovir concentrations. Monitor for evidence of tenofovir toxicity. (7.3)

USE IN SPECIFIC POPULATIONS

- Pregnancy: Women should avoid pregnancy while receiving ATRIPLA and for 12 weeks after discontinuation. (5.8)
- Nursing mothers: Women infected with HIV should be instructed not to breast feed. (8.3)
- Hepatitis B or C coinfection or therapy with medications associated with liver toxicity: Use caution in patients with hepatic impairment. (5.10, 6.2, 8.6)
- Pediatrics: Safety and efficacy not established in patients less than 18 years of age. (2, 8.4)

FULL PRESCRIBING INFORMATION

WARNINGS: LACTIC ACIDOSIS/SEVERE HEPATOMEGALY WITH STEATOSIS and POST TREATMENT EXACERBATION OF HEPATITIS B

Lactic acidosis and severe hepatomegaly with steatosis, including fatal cases, have been reported with the use of nucleoside analogs, including tenofovir disoproxil fumarate, a component of ATRIPLA, in combination with other antiretrovirals [See Warnings and Precautions (5.1)].

ATRIPLA is not approved for the treatment of chronic hepatitis B virus (HBV) infection and the safety and efficacy of ATRIPLA have not been established in patients coinfected with HBV and HIV-1. Severe acute exacerbations of hepatitis B have been reported in patients who have discontinued EMTRIVA or VIREAD, which are components of ATRIPLA. Hepatic function should be monitored closely with both clinical and laboratory follow-up for at least several months in patients who are coinfected with HIV-1 and HBV and discontinue ATRIPLA. If appropriate, initiation of anti-hepatitis B therapy may be warranted [See Warnings and Precautions (5.2)].

1 INDICATIONS AND USAGE

ATRIPLA® is indicated for use alone as a complete regimen or in combination with other antiretroviral agents for the treatment of HIV-1 infection in adults.

DOSAGE AND ADMINISTRATION

Adults: The dose of ATRIPLA is one tablet once daily taken orally on an empty stomach. Dosing at bedtime may improve the tolerability of nervous system symptoms.

Pediatrics: ATRIPLA is not recommended for use in patients <18 years of age.

Renal Impairment: Because ATRIPLA is a fixed-dose combination, it should not be prescribed for patients requiring dosage adjustment such as those with moderate or severe renal impairment (creatinine clearance <50 mL/min).

3 DOSAGE FORMS AND STRENGTHS

ATRIPLA is available as tablets. Each tablet contains 600 mg of efavirenz, 200 mg of emtricitabine and 300 mg of tenofovir disoproxil fumarate (tenofovir DF, which is equivalent to 245 mg of tenofovir disoproxil). The tablets are pink, capsule-shaped, film-coated, debossed with "123" on one side and plain-faced on the other side.

CONTRAINDICATIONS

4.1 Hypersensitivity

ATRIPLA is contraindicated in patients with previously demonstrated clinically significant hypersensitivity (e.g., Stevens-Johnson syndrome, erythema multiforme, or toxic skin eruptions) to efavirenz, a component of ATRIPLA.

4.2 Contraindicated Drugs

For some drugs, competition for CYP3A by efavirenz could result in inhibition of their metabolism and create the potential for serious and/or life-threatening adverse reactions (e.g., cardiac arrhythmias, prolonged sedation, or respiratory depression). Drugs that are contraindicated with ATRIPLA are listed in Table 1.

Table 1 Drugs That Are Contraindicated or Not Recommended for Use With ATRIPLA
Drug Class: Drug Name | Clinical Comment
Antifungal: voriconazole | Efavirenz significantly decreases voriconazole plasma concentrations, and coadministration may decrease the therapeutic effectiveness of voriconazole. Also, voriconazole significantly increases efavirenz plasma concentrations, which may increase the risk of efavirenz-associated side effects. Because ATRIPLA is a fixed-dose combination product, the dose of efavirenz cannot be altered. [See Clinical Pharmacology (12.3) Tables 5 and 6]
Ergot derivatives (dihydroergotamine, ergonovine, ergotamine, methylergonovine) | Potential for serious and/or life-threatening reactions such as acute ergot toxicity characterized by peripheral vasospasm and ischemia of the extremities and other tissues.
Benzodiazepines: midazolam, triazolam | Potential for serious and/or life-threatening reactions such as prolonged or increased sedation or respiratory depression.
Calcium channel blocker: bepridil | Potential for serious and/or life-threatening reactions such as cardiac arrhythmias.
GI motility agent: cisapride | Potential for serious and/or life-threatening reactions such as cardiac arrhythmias.
Neuroleptic: pimozide | Potential for serious and/or life-threatening reactions such as cardiac arrhythmias.
St. John's wort (Hypericum perforatum) | May lead to loss of virologic response and possible resistance to efavirenz or to the class of non-nucleoside reverse transcriptase inhibitors (NNRTIs).

WARNINGS AND PRECAUTIONS

5.1 Lactic Acidosis/Severe Hepatomegaly with Steatosis

Lactic acidosis and severe hepatomegaly with steatosis, including fatal cases, have been reported with the use of nucleoside analogs including tenofovir DF, a component of ATRIPLA, in combination with other antiretrovirals. A majority of these cases have been in women. Obesity and prolonged nucleoside exposure may be risk factors. Particular caution should be exercised when administering nucleoside analogs to any patient with known risk factors for liver disease; however, cases have also been reported in patients with no known risk factors. Treatment with ATRIPLA should be suspended in any patient who develops clinical or laboratory findings suggestive of lactic acidosis or pronounced hepatotoxicity (which may include hepatomegaly and steatosis even in the absence of marked transaminase elevations).

5.2 Patients Coinfected with HIV-1 and HBV

It is recommended that all patients with HIV-1 be tested for the presence of chronic HBV before initiating antiretroviral therapy. ATRIPLA is not approved for the treatment of chronic HBV infection, and the safety and efficacy of ATRIPLA have not been established in patients coinfected with HBV and HIV-1. Severe acute exacerbations of hepatitis B have been reported in patients who are coinfected with HBV and HIV-1 and have discontinued emtricitabine or tenofovir DF, two of the components of ATRIPLA. In some patients infected with HBV and treated with emtricitabine, the exacerbations of hepatitis B were associated with liver decompensation and liver failure. Patients who are coinfected with HIV-1 and HBV should be closely monitored with both clinical and laboratory follow up for at least several months after stopping treatment with ATRIPLA. If appropriate, initiation of anti-hepatitis B therapy may be warranted.

ATRIPLA should not be administered with HEPSERA® (adefovir dipivoxil) [See Drug Interactions (7.2)].

5.3 Drug Interactions

Efavirenz plasma concentrations may be altered by substrates, inhibitors, or inducers of CYP3A. Likewise, efavirenz may alter plasma concentrations of drugs metabolized by CYP3A [See Contraindications (4.2), Drug Interactions (7.1)].

5.4 Coadministration with Related Products

Related drugs not for coadministration with ATRIPLA include EMTRIVA (emtricitabine), VIREAD (tenofovir DF), TRUVADA (emtricitabine/tenofovir DF), and SUSTIVA (efavirenz), which contain the same active components as ATRIPLA. Due to similarities between emtricitabine and lamivudine, ATRIPLA should not be coadministered with drugs containing lamivudine, including Combivir (lamivudine/zidovudine), Epivir, or Epivir-HBV (lamivudine), Epzicom (abacavir sulfate/lamivudine), or Trizivir (abacavir sulfate/lamivudine/zidovudine).

5.5 Psychiatric Symptoms

Serious psychiatric adverse experiences have been reported in patients treated with efavirenz. In controlled trials of 1008 subjects treated with regimens containing efavirenz for a mean of 2.1 years and 635 subjects treated with control regimens for a mean of 1.5 years, the frequency (regardless of causality) of specific serious psychiatric events among subjects who received efavirenz or control regimens, respectively, were: severe depression (2.4%, 0.9%), suicidal ideation (0.7%, 0.3%), nonfatal suicide attempts (0.5%, 0%), aggressive behavior (0.4%, 0.5%), paranoid reactions (0.4%, 0.3%), and manic reactions (0.2%, 0.3%). When psychiatric symptoms similar to those noted above were combined and evaluated as a group in a multifactorial analysis of data from Study AI266006 (006), treatment with efavirenz was associated with an increase in the occurrence of these selected psychiatric symptoms. Other factors associated with an increase in the occurrence of these psychiatric symptoms were history of injection drug use, psychiatric history, and receipt of psychiatric medication at study entry; similar associations were observed in both the efavirenz and control treatment groups. In Study 006, onset of new serious psychiatric symptoms occurred throughout the study for both efavirenz-treated and control-treated subjects. One percent of efavirenz-treated subjects discontinued or interrupted treatment because of one or more of these selected psychiatric symptoms. There have also been occasional postmarketing reports of death by suicide, delusions, and psychosis-like behavior, although a causal relationship to the use of efavirenz cannot be determined from these reports. Patients with serious psychiatric adverse experiences should seek immediate medical evaluation to assess the possibility that the symptoms may be related to the use of efavirenz, and if so, to determine whether the risks of continued therapy outweigh the benefits [See Adverse Reactions (6)].

5.6 Nervous System Symptoms

Fifty-three percent (531/1008) of subjects receiving efavirenz in controlled trials reported central nervous system symptoms (any grade, regardless of causality) compared to 25% (156/635) of subjects receiving control regimens. These symptoms included dizziness (28.1% of the 1008 subjects), insomnia (16.3%), impaired concentration (8.3%), somnolence (7.0%), abnormal dreams (6.2%), and hallucinations (1.2%). Other reported symptoms were euphoria, confusion, agitation, amnesia, stupor, abnormal thinking, and depersonalization. The majority of these symptoms were mild-moderate (50.7%); symptoms were severe in 2.0% of subjects. Overall, 2.1% of subjects discontinued therapy as a result. These symptoms usually begin during the first or second day of therapy and generally resolve after the first 2–4 weeks of therapy. After 4 weeks of therapy, the prevalence of nervous system symptoms of at least moderate severity ranged from 5% to 9% in subjects treated with regimens containing efavirenz and from 3% to 5% in subjects treated with a control regimen. Patients should be informed that these common symptoms were likely to improve with continued therapy and were not predictive of subsequent onset of the less frequent psychiatric symptoms [See Warnings and Precautions (5.5)]. Dosing at bedtime may improve the tolerability of these nervous system symptoms [See Dosage and Administration (2)].

Analysis of long-term data from Study 006, (median follow-up 180 weeks, 102 weeks, and 76 weeks for subjects treated with efavirenz + zidovudine + lamivudine, efavirenz + indinavir, and indinavir + zidovudine + lamivudine, respectively) showed that, beyond 24 weeks of therapy, the incidences of new-onset nervous system symptoms among efavirenz-treated subjects were generally similar to those in the indinavir-containing control arm.

Patients receiving ATRIPLA should be alerted to the potential for additive central nervous system effects when ATRIPLA is used concomitantly with alcohol or psychoactive drugs.

Patients who experience central nervous system symptoms such as dizziness, impaired concentration, and/or drowsiness should avoid potentially hazardous tasks such as driving or operating machinery.

5.7 New Onset or Worsening Renal Impairment

Emtricitabine and tenofovir are principally eliminated by the kidney; however, efavirenz is not. Since ATRIPLA is a combination product and the dose of the individual components cannot be altered, patients with creatinine clearance <50 mL/min should not receive ATRIPLA.

Renal impairment, including cases of acute renal failure and Fanconi syndrome (renal tubular injury with severe hypophosphatemia), has been reported with the use of tenofovir DF [See Adverse Reactions (6.3)].

It is recommended that creatinine clearance be calculated in all patients prior to initiating therapy and as clinically appropriate during therapy with ATRIPLA. Routine monitoring of calculated creatinine clearance and serum phosphorus should be performed in patients at risk for renal impairment, including patients who have previously experienced renal events while receiving HEPSERA.

ATRIPLA should be avoided with concurrent or recent use of a nephrotoxic agent.

Pregnancy Category D: Efavirenz may cause fetal harm when administered during the first trimester to a pregnant woman. Pregnancy should be avoided in women receiving ATRIPLA. Barrier contraception must always be used in combination with other methods of contraception (e.g., oral or other hormonal contraceptives). Because of the long half-life of efavirenz, use of adequate contraceptive measures for 12 weeks after discontinuation of ATRIPLA is recommended. Women of childbearing potential should undergo pregnancy testing before initiation of ATRIPLA. If this drug is used during the first trimester of pregnancy, or if the patient becomes pregnant while taking this drug, the patient should be apprised of the potential harm to the fetus.

There are no adequate and well-controlled studies of ATRIPLA in pregnant women. ATRIPLA should be used during pregnancy only if the potential benefit justifies the potential risk to the fetus, such as in pregnant women without other therapeutic options.

Antiretroviral Pregnancy Registry: To monitor fetal outcomes of pregnant women, an Antiretroviral Pregnancy Registry has been established. Physicians are encouraged to register patients who become pregnant by calling (800) 258-4263.

TERATOGENIC EFFECTS

Efavirenz: As of July 2008, the Antiretroviral Pregnancy Registry has received prospective reports of 526 pregnancies exposed to efavirenz-containing regimens, nearly all of which were first-trimester exposures (507 pregnancies). Birth defects occurred in 13 of 407 live births (first-trimester exposure) and 2 of 37 live births (second/third-trimester exposure). One of these prospectively reported defects with first-trimester exposure was a neural tube defect. A single case of anophthalmia with first-trimester exposure to efavirenz has also been prospectively reported; however, this case included severe oblique facial clefts and amniotic banding, a known association with anophthalmia. There have been five retrospective reports of findings consistent with neural tube defects, including meningomyelocele. All mothers were exposed to efavirenz-containing regimens in the first trimester. Although a causal relationship of these events to the use of efavirenz has not been established, similar defects have been observed in preclinical studies of efavirenz.

Malformations have been observed in 3 of 20 fetuses/infants from efavirenz-treated cynomolgus monkeys (versus 0 of 20 concomitant controls) in a developmental toxicity study. The pregnant monkeys were dosed throughout pregnancy (postcoital days 20–150) with efavirenz 60 mg/kg daily, a dose which resulted in plasma drug concentrations similar to those in humans given 600 mg/day of efavirenz. Anencephaly and unilateral anophthalmia were observed in one fetus, microophthalmia was observed in another fetus, and cleft palate was observed in a third fetus. Efavirenz crosses the placenta in cynomolgus monkeys and produces fetal blood concentrations similar to maternal blood concentrations. Efavirenz has been shown to cross the placenta in rats and rabbits and produces fetal blood concentrations of efavirenz similar to maternal concentrations. An increase in fetal resorptions was observed in rats at efavirenz doses that produced peak plasma concentrations and AUC values in female rats equivalent to or lower than those achieved in humans given 600 mg once daily of efavirenz. Efavirenz produced no reproductive toxicities when given to pregnant rabbits at doses that produced peak plasma concentrations similar to and AUC values approximately half of those achieved in humans given 600 mg once daily of efavirenz.

5.9 Rash

In controlled clinical trials, 26% (266/1008) of subjects treated with 600 mg efavirenz experienced new-onset skin rash compared with 17% (111/635) of subjects treated in control groups. Rash associated with blistering, moist desquamation, or ulceration occurred in 0.9% (9/1008) of subjects treated with efavirenz. The incidence of Grade 4 rash (e.g., erythema multiforme, Stevens-Johnson syndrome) in subjects treated with efavirenz in all studies and expanded access was 0.1%. Rashes are usually mild-to-moderate maculopapular skin eruptions that occur within the first 2 weeks of initiating therapy with efavirenz (median time to onset of rash in adults was 11 days) and, in most subjects continuing therapy with efavirenz, rash resolves within 1 month (median duration, 16 days). The discontinuation rate for rash in clinical trials was 1.7% (17/1008). ATRIPLA can be reinitiated in patients interrupting therapy because of rash. ATRIPLA should be discontinued in patients developing severe rash associated with blistering, desquamation, mucosal involvement, or fever. Appropriate antihistamines and/or corticosteroids may improve the tolerability and hasten the resolution of rash.

Experience with efavirenz in subjects who discontinued other antiretroviral agents of the NNRTI class is limited. Nineteen subjects who discontinued nevirapine because of rash have been treated with efavirenz. Nine of these subjects developed mild-to-moderate rash while receiving therapy with efavirenz, and two of these subjects discontinued because of rash.

5.10 Liver Enzymes

In patients with known or suspected history of hepatitis B or C infection and in patients treated with other medications associated with liver toxicity, monitoring of liver enzymes is recommended [See also Warnings and Precautions (5.2)]. In patients with persistent elevations of serum transaminases to greater than five times the upper limit of the normal range, the benefit of continued therapy with ATRIPLA needs to be weighed against the unknown risks of significant liver toxicity [See Adverse Reactions (6.2)].

5.11 Decreases in Bone Mineral Density

Bone mineral density (BMD) monitoring should be considered for HIV-1 infected subjects who have a history of pathologic bone fracture or are at risk for osteopenia. Although the effect of supplementation with calcium and vitamin D was not studied, such supplementation may be beneficial for all patients. If bone abnormalities are suspected then appropriate consultation should be obtained.

In a 144-week study of treatment-naive subjects receiving tenofovir DF, decreases in BMD were seen at the lumbar spine and hip in both arms of the study. At Week 144, there was a significantly greater mean percentage decrease from baseline in BMD at the lumbar spine in subjects receiving tenofovir DF + lamivudine + efavirenz compared with subjects receiving stavudine + lamivudine + efavirenz. Changes in BMD at the hip were similar between the two treatment groups. In both groups, the majority of the reduction in BMD occurred in the first 24–48 weeks of the study and this reduction was sustained through 144 weeks. Twenty-eight percent of tenofovir DF-treated subjects vs. 21% of the comparator subjects lost at least 5% of BMD at the spine or 7% of BMD at the hip. Clinically relevant fractures (excluding fingers and toes) were reported in 4 subjects in the tenofovir DF group and 6 subjects in the comparator group. Tenofovir DF was associated with significant increases in biochemical markers of bone metabolism (serum bone-specific alkaline phosphatase, serum osteocalcin, serum C-telopeptide, and urinary N-telopeptide), suggesting increased bone turnover. Serum parathyroid hormone levels and 1,25 Vitamin D levels were also higher in subjects receiving tenofovir DF. The effects of tenofovir DF-associated changes in BMD and biochemical markers on long-term bone health and future fracture risk are unknown. For additional information, consult the tenofovir DF prescribing information.

Cases of osteomalacia (associated with proximal renal tubulopathy and which may contribute to fractures) have been reported in association with the use of tenofovir DF [See Adverse Reactions (6.3)].

5.12 Convulsions

Convulsions have been observed in patients receiving efavirenz, generally in the presence of known medical history of seizures. Caution must be taken in any patient with a history of seizures.

Patients who are receiving concomitant anticonvulsant medications primarily metabolized by the liver, such as phenytoin and phenobarbital, may require periodic monitoring of plasma levels [See Drug Interactions (7.3)].

5.13 Immune Reconstitution Syndrome

Immune reconstitution syndrome has been reported in patients treated with combination antiretroviral therapy, including the components of ATRIPLA. During the initial phase of combination antiretroviral treatment, patients whose immune system responds may develop an inflammatory response to indolent or residual opportunistic infections [such as Mycobacterium avium infection, cytomegalovirus, Pneumocystis jirovecii pneumonia (PCP), or tuberculosis], which may necessitate further evaluation and treatment.

5.14 Fat Redistribution

Redistribution/accumulation of body fat including central obesity, dorsocervical fat enlargement (buffalo hump), peripheral wasting, facial wasting, breast enlargement, and "cushingoid appearance" have been observed in patients receiving antiretroviral therapy. The mechanism and long-term consequences of these events are currently unknown. A causal relationship has not been established.

ADVERSE REACTIONS

Efavirenz, Emtricitabine and Tenofovir Disoproxil Fumarate: The following adverse reactions are discussed in other sections of the labeling:

- Lactic Acidosis/Severe Hepatomegaly with Steatosis [See Boxed Warning, Warnings and Precautions (5.1)].
- Severe Acute Exacerbations of Hepatitis B [See Boxed Warning, Warnings and Precautions (5.2)].
- Psychiatric Symptoms [See Warnings and Precautions (5.5)].
- Nervous System Symptoms [See Warnings and Precautions (5.6)].
- New Onset or Worsening Renal Impairment [See Warnings and Precautions (5.7)].
- Rash [See Warnings and Precautions (5.9)].
- Decreases in Bone Mineral Density [See Warnings and Precautions (5.11)].
- Immune Reconstitution Syndrome [See Warnings and Precautions (5.13)].
- Drug Interactions [See Contraindications (4.2), Warnings and Precautions (5.3) and Drug Interactions (7)].

For additional safety information about SUSTIVA (efavirenz), EMTRIVA (emtricitabine), or VIREAD (tenofovir DF) in combination with other antiretroviral agents, consult the prescribing information for these products.

6.1 Adverse Reactions from Clinical Trials Experience

Because clinical trials are conducted under widely varying conditions, adverse reaction rates observed in the clinical trials of a drug cannot be directly compared to rates in the clinical trials of another drug and may not reflect the rates observed in practice.

Study 934

Study 934 was an open-label active-controlled study in which 511 antiretroviral-naive subjects received either emtricitabine + tenofovir DF administered in combination with efavirenz (N=257) or zidovudine/lamivudine administered in combination with efavirenz (N=254).

The most common adverse reactions (incidence ≥ 10%, any severity) occurring in Study 934 include diarrhea, nausea, fatigue, headache, dizziness, depression, insomnia, abnormal dreams, and rash. Adverse reactions observed in Study 934 were generally consistent with those seen in previous studies of the individual components (Table 2).

Table 2 Selected Treatment-Emergent Adverse Reactions [Frequencies of adverse reactions are based on all treatment-emergent adverse events, regardless of relationship to study drug.] (Grades 2–4) Reported in ≥5% in Either Treatment Group in Study 934 (0–144 Weeks)
 | FTC + TDF + EFV [From Weeks 96 to 144 of the study, subjects received emtricitabine/tenofovir DF administered in combination with efavirenz in place of emtricitabine + tenofovir DF with efavirenz.] | AZT/3TC + EFV
 | N=257 | N=254
Gastrointestinal Disorder
Diarrhea | 9% | 5%
Nausea | 9% | 7%
Vomiting | 2% | 5%
General Disorders and Administration Site Condition
Fatigue | 9% | 8%
Infections and Infestations
Sinusitis | 8% | 4%
Upper respiratory tract infections | 8% | 5%
Nasopharyngitis | 5% | 3%
Nervous System Disorders
Headache | 6% | 5%
Dizziness | 8% | 7%
Psychiatric Disorders
Anxiety | 5% | 4%
Depression | 9% | 7%
Insomnia | 5% | 7%
Skin and Subcutaneous Tissue Disorders
Rash Event [Rash event includes rash, exfoliative rash, rash generalized, rash macular, rash maculo-papular, rash pruritic, and rash vesicular.] | 7% | 9%

Study 073

In Study 073, subjects with stable, virologic suppression on antiretroviral therapy and no history of virologic failure were randomized to receive ATRIPLA or to stay on their baseline regimen. The adverse reactions observed in Study 073 were generally consistent with those seen in Study 934 and those seen with the individual components of ATRIPLA when each was administered in combination with other antiretroviral agents.

Efavirenz, Emtricitabine, or Tenofovir Disoproxil Fumarate

In addition to the adverse reactions in Study 934 and Study 073 the following adverse reactions were observed in clinical trials of efavirenz, emtricitabine, or tenofovir DF in combination with other antiretroviral agents.

Efavirenz: The most significant adverse reactions observed in subjects treated with efavirenz are nervous system symptoms [See Warnings and Precautions (5.6)], psychiatric symptoms [See Warnings and Precautions (5.5)], and rash [See Warnings and Precautions (5.9)].

Selected adverse reactions of moderate-severe intensity observed in ≥2% of efavirenz-treated subjects in two controlled clinical trials included pain, impaired concentration, abnormal dreams, somnolence, anorexia, dyspepsia, abdominal pain, nervousness, and pruritus.

Pancreatitis has also been reported, although a causal relationship with efavirenz has not been established. Asymptomatic increases in serum amylase levels were observed in a significantly higher number of subjects treated with efavirenz 600 mg than in control subjects.

Emtricitabine and Tenofovir Disoproxil Fumarate: Adverse reactions that occurred in at least 5% of treatment-experienced or treatment-naive subjects receiving emtricitabine or tenofovir DF with other antiretroviral agents in clinical trials include arthralgia, increased cough, dyspepsia, fever, myalgia, pain, abdominal pain, back pain, paresthesia, peripheral neuropathy (including peripheral neuritis and neuropathy), pneumonia, rhinitis and rash event (including rash, pruritus, maculopapular rash, urticaria, vesiculobullous rash, pustular rash and allergic reaction).

Skin discoloration has been reported with higher frequency among emtricitabine-treated subjects; it was manifested by hyperpigmentation on the palms and/or soles and was generally mild and asymptomatic. The mechanism and clinical significance are unknown.

Efavirenz, Emtricitabine and Tenofovir Disoproxil Fumarate: Laboratory abnormalities observed in Study 934 were generally consistent with those seen in previous studies (Table 3).

Table 3 Significant Laboratory Abnormalities Reported in ≥1% of Subjects in Either Treatment Group in Study 934 (0–144 Weeks)
 | FTC + TDF + EFV [From Weeks 96 to 144 of the study, subjects received emtricitabine/tenofovir DF administered in combination with efavirenz in place of emtricitabine + tenofovir DF with efavirenz.] | AZT/3TC + EFV
 | N=257 | N=254
Any ≥ Grade 3 Laboratory Abnormality | 30% | 26%
Fasting Cholesterol (>240 mg/dL) | 22% | 24%
Creatine Kinase (M: >990 U/L) (F: >845 U/L) | 9% | 7%
Serum Amylase (>175 U/L) | 8% | 4%
Alkaline Phosphatase (>550 U/L) | 1% | 0%
AST (M: >180 U/L) (F: >170 U/L) | 3% | 3%
ALT (M: >215 U/L) (F: >170 U/L) | 2% | 3%
Hemoglobin (<8.0 mg/dL) | 0% | 4%
Hyperglycemia (>250 mg/dL) | 2% | 1%
Hematuria (>75 RBC/HPF) | 3% | 2%
Glycosuria (≥3+) | <1% | 1%
Neutrophils (<750/mm^3) | 3% | 5%
Fasting Triglycerides (>750 mg/dL) | 4% | 2%

Laboratory abnormalities observed in Study 073 were generally consistent with those in Study 934.

In addition to the laboratory abnormalities described for Study 934 (Table 3), Grade 3/4 elevations of bilirubin (>2.5 × ULN), pancreatic amylase (>2.0 × ULN), serum glucose (<40 or >250 mg/dL), and serum lipase (>2.0 × ULN) occurred in up to 3% of subjects treated with emtricitabine or tenofovir DF with other antiretroviral agents in clinical trials.

Hepatic Events: In Study 934, 19 subjects treated with efavirenz, emtricitabine, and tenofovir DF and 20 subjects treated with efavirenz and fixed-dose zidovudine/lamivudine were hepatitis B surface antigen or hepatitis C antibody positive. Among these coinfected subjects, one subject (1/19) in the efavirenz, emtricitabine and tenofovir DF arm had elevations in transaminases to greater than five times ULN through 144 weeks. In the fixed-dose zidovudine/lamivudine arm, two subjects (2/20) had elevations in transaminases to greater than five times ULN through 144 weeks. No HBV and/or HCV coinfected subject discontinued from the study due to hepatobiliary disorders [See Warnings and Precautions (5.10)].

6.3 Postmarketing Experience

The following adverse reactions have been identified during postapproval use of efavirenz, emtricitabine, or tenofovir DF. Because postmarketing reactions are reported voluntarily from a population of uncertain size, it is not always possible to reliably estimate their frequency or establish a causal relationship to drug exposure.

Efavirenz:

Cardiac Disorders
Palpitations

Ear and Labyrinth Disorders
Tinnitus

Endocrine Disorders
Gynecomastia

Eye Disorders
Abnormal vision

Gastrointestinal Disorders
Constipation, malabsorption

General Disorders and Administration Site Conditions
Asthenia

Hepatobiliary Disorders
Hepatic enzyme increase, hepatic failure, hepatitis

Immune System Disorders
Allergic reactions

Metabolism and Nutrition Disorders
Redistribution/accumulation of body fat [See Warnings and Precautions (5.14)], hypercholesterolemia, hypertriglyceridemia

Musculoskeletal and Connective Tissue Disorders
Arthralgia, myalgia, myopathy

Nervous System Disorders
Abnormal coordination, ataxia, cerebellar coordination and balance disturbances, convulsions, hypoesthesia, paresthesia, neuropathy, tremor

Psychiatric Disorders
Aggressive reactions, agitation, delusions, emotional lability, mania, neurosis, paranoia, psychosis, suicide

Respiratory, Thoracic and Mediastinal Disorders
Dyspnea

Skin and Subcutaneous Tissue Disorders
Flushing, erythema multiforme, photoallergic dermatitis, Stevens-Johnson syndrome

Emtricitabine: No postmarketing adverse reactions have been identified for inclusion in this section.

Tenofovir Disoproxil Fumarate:

Immune System Disorders
Allergic reaction, including angioedema

Metabolism and Nutrition Disorders
Lactic acidosis, hypokalemia, hypophosphatemia

Respiratory, Thoracic, and Mediastinal Disorders
Dyspnea

Gastrointestinal Disorders
Pancreatitis, increased amylase, abdominal pain

Hepatobiliary Disorders
Hepatic steatosis, hepatitis, increased liver enzymes (most commonly AST, ALT, gamma GT)

Skin and Subcutaneous Tissue Disorders
Rash

Musculoskeletal and Connective Tissue Disorders
Rhabdomyolysis, osteomalacia (manifested as bone pain and which may contribute to fractures), muscular weakness, myopathy

Renal and Urinary Disorders
Acute renal failure, renal failure, acute tubular necrosis, Fanconi syndrome, proximal renal tubulopathy, interstitial nephritis (including acute cases), nephrogenic diabetes insipidus, renal insufficiency, increased creatinine, proteinuria, polyuria

General Disorders and Administration Site Conditions
Asthenia

The following adverse reactions, listed under the body system headings above, may occur as a consequence of proximal renal tubulopathy: rhabdomyolysis, osteomalacia, hypokalemia, muscular weakness, myopathy, hypophosphatemia.

7 DRUG INTERACTIONS

This section describes clinically relevant drug interactions with ATRIPLA. Drug interaction studies are described elsewhere in the labeling [see Clinical Pharmacology (12.3)].

7.1 Efavirenz

Efavirenz has been shown in vivo to induce CYP3A. Other compounds that are substrates of CYP3A may have decreased plasma concentrations when coadministered with efavirenz. In vitro studies have demonstrated that efavirenz inhibits CYP2C9, 2C19, and 3A4 isozymes in the range of observed efavirenz plasma concentrations. Coadministration of efavirenz with drugs primarily metabolized by these isozymes may result in altered plasma concentrations of the coadministered drug. Therefore, appropriate dose adjustments may be necessary for these drugs.

Drugs that induce CYP3A activity (e.g., phenobarbital, rifampin, rifabutin) would be expected to increase the clearance of efavirenz resulting in lowered plasma concentrations.

7.2 Emtricitabine and Tenofovir Disoproxil Fumarate

Since emtricitabine and tenofovir are primarily eliminated by the kidneys, coadministration of ATRIPLA with drugs that reduce renal function or compete for active tubular secretion may increase serum concentrations of emtricitabine, tenofovir, and/or other renally eliminated drugs. Some examples include, but are not limited to, acyclovir, adefovir dipivoxil, cidofovir, ganciclovir, valacyclovir, and valganciclovir.

Coadministration of tenofovir DF and didanosine should be undertaken with caution and patients receiving this combination should be monitored closely for didanosine-associated adverse reactions. Didanosine should be discontinued in patients who develop didanosine-associated adverse reactions [for didanosine dosing adjustment recommendations, see Table 4]. Suppression of CD4^+ cell counts has been observed in patients receiving tenofovir DF with didanosine 400 mg daily.

Lopinavir/ritonavir has been shown to increase tenofovir concentrations. The mechanism of this interaction is unknown. Patients receiving lopinavir/ritonavir with ATRIPLA should be monitored for tenofovir-associated adverse reactions. ATRIPLA should be discontinued in patients who develop tenofovir-associated adverse reactions [See Table 4].

Coadministration of atazanavir with ATRIPLA is not recommended since coadministration of atazanavir with either efavirenz or tenofovir DF has been shown to decrease plasma concentrations of atazanavir. Also, atazanavir has been shown to increase tenofovir concentrations. There are insufficient data to support dosing recommendations for atazanavir or atazanavir/ritonavir in combination with ATRIPLA [See Table 4].

7.3 Efavirenz, Emtricitabine and Tenofovir Disoproxil Fumarate

Other important drug interaction information for ATRIPLA is summarized in Table 1 and Table 4. The drug interactions described are based on studies conducted with efavirenz, emtricitabine or tenofovir DF as individual agents or are potential drug interactions; no drug interaction studies have been conducted using ATRIPLA [for pharmacokinetics data see Clinical Pharmacology (12.3), Tables 5–9]. The tables include potentially significant interactions, but are not all inclusive.

Table 4 Established and Other Potentially Significant [This table is not all inclusive.] Drug Interactions: Alteration in Dose or Regimen May Be Recommended Based on Drug Interaction Studies or Predicted Interaction
Concomitant Drug Class: Drug Name | Effect | Clinical Comment
Antiretroviral agents
Protease inhibitor: atazanavir | ↓atazanavir concentration ↑ tenofovir concentration | Coadministration of atazanavir with ATRIPLA is not recommended. Coadministration of atazanavir with either efavirenz or tenofovir DF decreases plasma concentrations of atazanavir. The combined effect of efavirenz plus tenofovir DF on atazanavir plasma concentrations is not known. Also, atazanavir has been shown to increase tenofovir concentrations. There are insufficient data to support dosing recommendations for atazanavir or atazanavir/ritonavir in combination with ATRIPLA.
Protease inhibitor: fosamprenavir calcium | ↓ amprenavir concentration | Fosamprenavir (unboosted): Appropriate doses of fosamprenavir and ATRIPLA with respect to safety and efficacy have not been established. Fosamprenavir/ritonavir: An additional 100 mg/day (300 mg total) of ritonavir is recommended when ATRIPLA is administered with fosamprenavir/ritonavir once daily. No change in the ritonavir dose is required when ATRIPLA is administered with fosamprenavir plus ritonavir twice daily.
Protease inhibitor: indinavir | ↓ indinavir concentration | The optimal dose of indinavir, when given in combination with efavirenz, is not known. Increasing the indinavir dose to 1000 mg every 8 hours does not compensate for the increased indinavir metabolism due to efavirenz.
Protease inhibitor: lopinavir/ritonavir | ↓ lopinavir concentration ↑ tenofovir concentration | A dose increase of lopinavir/ritonavir to 600/150 mg (3 tablets) twice daily may be considered when used in combination with efavirenz in treatment-experienced patients where decreased susceptibility to lopinavir is clinically suspected (by treatment history or laboratory evidence). Patients should be monitored for tenofovir-associated adverse reactions. ATRIPLA should be discontinued in patients who develop tenofovir-associated adverse reactions.
Protease inhibitor: ritonavir | ↑ ritonavir concentration ↑ efavirenz concentration | When ritonavir 500 mg every 12 hours was coadministered with efavirenz 600 mg once daily, the combination was associated with a higher frequency of adverse clinical experiences (e.g., dizziness, nausea, paresthesia) and laboratory abnormalities (elevated liver enzymes). Monitoring of liver enzymes is recommended when ATRIPLA is used in combination with ritonavir.
Protease inhibitor: saquinavir | ↓ saquinavir concentration | Should not be used as sole protease inhibitor in combination with ATRIPLA.
NRTI: didanosine | ↑ didanosine concentration | Higher didanosine concentrations could potentiate didanosine-associated adverse reactions, including pancreatitis and neuropathy. In adults weighing >60 kg, the didanosine dose should be reduced to 250 mg if coadministered with ATRIPLA. Data are not available to recommend a dose adjustment of didanosine for patients weighing <60 kg. Coadministration of ATRIPLA and didanosine should be undertaken with caution and patients receiving this combination should be monitored closely for didanosine-associated adverse reactions. For additional information, please consult the Videx / Videx EC (didanosine) prescribing information.
Other agents
Anticoagulant: warfarin | ↑ or ↓ warfarin concentration | Plasma concentrations and effects potentially increased or decreased by efavirenz.
Anticonvulsants: carbamazepine | ↓ carbamazepine concentration ↓ efavirenz concentration | There are insufficient data to make a dose recommendation for ATRIPLA. Alternative anticonvulsant treatment should be used.
phenytoin phenobarbital | ↓ anticonvulsant concentration ↓ efavirenz concentration | Potential for reduction in anticonvulsant and/or efavirenz plasma levels; periodic monitoring of anticonvulsant plasma levels should be conducted.
Antidepressant: sertraline | ↓ sertraline concentration | Increases in sertraline dose should be guided by clinical response.
Antifungals: itraconazole | ↓ itraconazole concentration ↓ hydroxy-itraconazole concentration | Since no dose recommendation for itraconazole can be made, alternative antifungal treatment should be considered.
ketoconazole | ↓ ketoconazole concentration | Drug interaction studies with ATRIPLA and ketoconazole have not been conducted. Efavirenz has the potential to decrease plasma concentrations of ketoconazole.
Anti-infective: clarithromycin | ↓ clarithromycin concentration ↑ 14-OH metabolite concentration | Clinical significance unknown. In uninfected volunteers, 46% developed rash while receiving efavirenz and clarithromycin. No dose adjustment of ATRIPLA is recommended when given with clarithromycin. Alternatives to clarithromycin, such as azithromycin, should be considered. Other macrolide antibiotics, such as erythromycin, have not been studied in combination with ATRIPLA.
Antimycobacterial: rifabutin | ↓ rifabutin concentration | Increase daily dose of rifabutin by 50%. Consider doubling the rifabutin dose in regimens where rifabutin is given 2 or 3 times a week.
Antimycobacterial: rifampin | ↓ efavirenz concentration | Clinical significance of reduced efavirenz concentration is unknown. Dosing recommendations for concomitant use of ATRIPLA and rifampin have not been established.
Calcium channel blockers: diltiazem | ↓ diltiazem concentration ↓ desacetyl diltiazem concentration ↓ N-monodes-methyl diltiazem concentration | Diltiazem dose adjustments should be guided by clinical response (refer to the prescribing information for diltiazem). No dose adjustment of ATRIPLA is necessary when administered with diltiazem.
Others (e.g., felodipine, nicardipine, nifedipine, verapamil) | ↓ calcium channel blocker | No data are available on the potential interactions of efavirenz with other calcium channel blockers that are substrates of CYP3A. The potential exists for reduction in plasma concentrations of the calcium channel blocker. Dose adjustments should be guided by clinical response (refer to the prescribing information for the calcium channel blocker).
HMG-CoA reductase inhibitors: atorvastatin pravastatin simvastatin | ↓ atorvastatin concentration ↓ pravastatin concentration ↓ simvastatin concentration | Plasma concentrations of atorvastatin, pravastatin, and simvastatin decreased with efavirenz. Consult the prescribing information for the HMG-CoA reductase inhibitor for guidance on individualizing the dose.
Hormonal contraceptives:
Oral: Ethinyl estradiol/Norgestimate | ↓ active metabolites of norgestimate | A reliable method of barrier contraception must be used in addition to hormonal contraceptives. Efavirenz had no effect on ethinyl estradiol concentrations, but progestin levels (norelgestromin and levonorgestrel) were markedly decreased. No effect of ethinyl estradiol/norgestimate on efavirenz plasma concentrations was observed.
Implant: Etonogestrel | ↓ etonogestrel | A reliable method of barrier contraception must be used in addition to hormonal contraceptives. The interaction between etonogestrel and efavirenz has not been studied. Decreased exposure of etonogestrel may be expected. There have been postmarketing reports of contraceptive failure with etonogestrel in efavirenz-exposed patients.
Immunosuppressants: Cyclosporine, tacrolimus, sirolimus, and others metabolized by CYP3A | ↓ immuno-suppressant | Decreased exposure of the immunosuppressant may be expected due to CYP3A induction by efavirenz. These immunosuppressants are not anticipated to affect exposure of efavirenz. Dose adjustments of the immunosuppressant may be required. Close monitoring of immunosuppressant concentrations for at least 2 weeks (until stable concentrations are reached) is recommended when starting or stopping treatment with ATRIPLA.
Narcotic analgesic: methadone | ↓ methadone concentration | Coadministration of efavirenz in HIV-1 infected individuals with a history of injection drug use resulted in decreased plasma levels of methadone and signs of opiate withdrawal. Methadone dose was increased by a mean of 22% to alleviate withdrawal symptoms. Patients should be monitored for signs of withdrawal and their methadone dose increased as required to alleviate withdrawal symptoms.

Cannabinoid Test Interaction: Efavirenz does not bind to cannabinoid receptors. False-positive urine cannabinoid test results have been observed in non-HIV-infected volunteers receiving efavirenz when the Microgenics Cedia DAU Multi-Level THC assay was used for screening. Negative results were obtained when more specific confirmatory testing was performed with gas chromatography/mass spectrometry. For more information, please consult the SUSTIVA prescribing information.

USE IN SPECIFIC POPULATIONS

8.1 Pregnancy

Pregnancy Category D [See Warnings and Precautions (5.8)]

8.3 Nursing Mothers

The Centers for Disease Control and Prevention recommend that HIV-1 infected mothers not breast-feed their infants to avoid risking postnatal transmission of HIV-1. Studies in rats have demonstrated that both efavirenz and tenofovir are secreted in milk. It is not known whether efavirenz, emtricitabine, or tenofovir is excreted in human milk. Because of both the potential for HIV-1 transmission and the potential for serious adverse reactions in nursing infants, mothers should be instructed not to breast-feed if they are receiving ATRIPLA.

8.4 Pediatric Use

ATRIPLA is not recommended for patients less than 18 years of age because it is a fixed-dose combination tablet containing a component, tenofovir DF, for which safety and efficacy have not been established in this age group.

8.5 Geriatric Use

Clinical studies of efavirenz, emtricitabine, or tenofovir DF did not include sufficient numbers of subjects aged 65 and over to determine whether they respond differently from younger subjects. In general, dose selection for the elderly patients should be cautious, keeping in mind the greater frequency of decreased hepatic, renal, or cardiac function, and of concomitant disease or other drug therapy.

8.6 Hepatic Impairment

The pharmacokinetics of efavirenz have not been adequately studied in subjects with hepatic impairment. Because of the extensive cytochrome P450-mediated metabolism of efavirenz and limited clinical experience in patients with hepatic impairment, caution should be exercised in administering ATRIPLA to these patients [See Warnings and Precautions (5.10)].

8.7 Renal Impairment

Because ATRIPLA is a fixed-dose combination, it should not be prescribed for patients requiring dosage adjustment such as those with moderate or severe renal impairment (creatinine clearance <50 mL/min) [See Warnings and Precautions (5.7)].

10 OVERDOSAGE

If overdose occurs, the patient should be monitored for evidence of toxicity, including monitoring of vital signs and observation of the patient's clinical status; standard supportive treatment should then be applied as necessary. Administration of activated charcoal may be used to aid removal of unabsorbed efavirenz. Hemodialysis can remove both emtricitabine and tenofovir DF (refer to detailed information below), but is unlikely to significantly remove efavirenz from the blood.

Efavirenz: Some patients accidentally taking 600 mg twice daily have reported increased nervous system symptoms. One patient experienced involuntary muscle contractions.

Emtricitabine: Limited clinical experience is available at doses higher than the therapeutic dose of emtricitabine. In one clinical pharmacology study single doses of emtricitabine 1200 mg were administered to 11 subjects. No severe adverse reactions were reported.

Hemodialysis treatment removes approximately 30% of the emtricitabine dose over a 3-hour dialysis period starting within 1.5 hours of emtricitabine dosing (blood flow rate of 400 mL/min and a dialysate flow rate of 600 mL/min). It is not known whether emtricitabine can be removed by peritoneal dialysis.

Tenofovir Disoproxil Fumarate: Limited clinical experience at doses higher than the therapeutic dose of tenofovir DF 300 mg is available. In one study, 600 mg tenofovir DF was administered to 8 subjects orally for 28 days, and no severe adverse reactions were reported. The effects of higher doses are not known.

Tenofovir is efficiently removed by hemodialysis with an extraction coefficient of approximately 54%. Following a single 300 mg dose of tenofovir DF, a 4-hour hemodialysis session removed approximately 10% of the administered tenofovir dose.

11 DESCRIPTION

ATRIPLA is a fixed-dose combination tablet containing efavirenz, emtricitabine, and tenofovir disoproxil fumarate (tenofovir DF). SUSTIVA is the brand name for efavirenz, a non-nucleoside reverse transcriptase inhibitor. EMTRIVA is the brand name for emtricitabine, a synthetic nucleoside analog of cytidine. VIREAD is the brand name for tenofovir DF, which is converted in vivo to tenofovir, an acyclic nucleoside phosphonate (nucleotide) analog of adenosine 5'-monophosphate. VIREAD and EMTRIVA are the components of TRUVADA.

ATRIPLA tablets are for oral administration. Each tablet contains 600 mg of efavirenz, 200 mg of emtricitabine, and 300 mg of tenofovir DF (which is equivalent to 245 mg of tenofovir disoproxil) as active ingredients. The tablets include the following inactive ingredients: croscarmellose sodium, hydroxypropyl cellulose, magnesium stearate, microcrystalline cellulose, and sodium lauryl sulfate. The tablets are film-coated with a coating material containing black iron oxide, polyethylene glycol, polyvinyl alcohol, red iron oxide, talc, and titanium dioxide.

Efavirenz: Efavirenz is chemically described as (S)-6-chloro-4-(cyclopropylethynyl)-1,4-dihydro-4-(trifluoromethyl)-2H-3,1-benzoxazin-2-one. Its molecular formula is C14H9ClF3NO2 and its structural formula is:

Efavirenz is a white to slightly pink crystalline powder with a molecular mass of 315.68. It is practically insoluble in water (<10 µg/mL).

Emtricitabine: The chemical name of emtricitabine is 5-fluoro-1-(2R,5S)-[2-(hydroxymethyl)-1,3-oxathiolan-5-yl]cytosine. Emtricitabine is the (-) enantiomer of a thio analog of cytidine, which differs from other cytidine analogs in that it has a fluorine in the 5-position.

It has a molecular formula of C8H10FN3O3S and a molecular weight of 247.24. It has the following structural formula:

Emtricitabine is a white to off-white crystalline powder with a solubility of approximately 112 mg/mL in water at 25 oC.

Tenofovir Disoproxil Fumarate: Tenofovir DF is a fumaric acid salt of the bis-isopropoxycarbonyloxymethyl ester derivative of tenofovir. The chemical name of tenofovir disoproxil fumarate is 9-[(R)-2[[bis[[(isopropoxycarbonyl)oxy]- methoxy]phosphinyl]methoxy]propyl]adenine fumarate (1:1). It has a molecular formula of C19H30N5O10P • C4H4O4 and a molecular weight of 635.52. It has the following structural formula:

Tenofovir DF is a white to off-white crystalline powder with a solubility of 13.4 mg/mL in water at 25 °C.

12 CLINICAL PHARMACOLOGY

For additional information on Mechanism of Action, Antiviral Activity, Resistance and Cross Resistance, please consult the SUSTIVA, EMTRIVA and VIREAD prescribing information.

12.1 Mechanism of Action

ATRIPLA is a fixed-dose combination of antiviral drugs efavirenz, emtricitabine and tenofovir disoproxil fumarate. [See Clinical Pharmacology (12.4)].

ATRIPLA: One ATRIPLA tablet is bioequivalent to one SUSTIVA tablet (600 mg) plus one EMTRIVA capsule (200 mg) plus one VIREAD tablet (300 mg) following single-dose administration to fasting healthy subjects (N=45).

Efavirenz: In HIV-1 infected subjects time-to-peak plasma concentrations were approximately 3–5 hours and steady-state plasma concentrations were reached in 6–10 days. In 35 HIV-1 infected subjects receiving efavirenz 600 mg once daily, steady-state Cmax was 12.9 ± 3.7 µM (mean ± SD), Cmin was 5.6 ± 3.2 μM, and AUC was 184 ± 73 µM∙hr. Efavirenz is highly bound (approximately 99.5–99.75%) to human plasma proteins, predominantly albumin. Following administration of ^14C-labeled efavirenz, 14–34% of the dose was recovered in the urine (mostly as metabolites) and 16–61% was recovered in feces (mostly as parent drug). In vitro studies suggest CYP3A and CYP2B6 are the major isozymes responsible for efavirenz metabolism. Efavirenz has been shown to induce CYP enzymes, resulting in induction of its own metabolism. Efavirenz has a terminal half-life of 52–76 hours after single doses and 40–55 hours after multiple doses.

Emtricitabine: Following oral administration, emtricitabine is rapidly absorbed with peak plasma concentrations occurring at 1–2 hours post-dose. Following multiple dose oral administration of emtricitabine to 20 HIV-1 infected subjects, the steady-state plasma emtricitabine Cmax was 1.8 ± 0.7 µg/mL (mean ± SD) and the AUC over a 24-hour dosing interval was 10.0 ± 3.1 µg∙hr/mL. The mean steady state plasma trough concentration at 24 hours post-dose was 0.09 µg/mL. The mean absolute bioavailability of emtricitabine was 93%. In vitro binding of emtricitabine to human plasma proteins is <4% and is independent of concentration over the range of 0.02–200 µg/mL. Following administration of radiolabelled emtricitabine, approximately 86% is recovered in the urine and 13% is recovered as metabolites. The metabolites of emtricitabine include 3'-sulfoxide diastereomers and their glucuronic acid conjugate. Emtricitabine is eliminated by a combination of glomerular filtration and active tubular secretion with a renal clearance in adults with normal renal function of 213 ± 89 mL/min (mean ± SD). Following a single oral dose, the plasma emtricitabine half-life is approximately 10 hours.

Tenofovir Disoproxil Fumarate: Following oral administration of a single 300 mg dose of tenofovir DF to HIV-1 infected subjects in the fasted state, maximum serum concentrations (Cmax) were achieved in 1.0 ± 0.4 hrs (mean ± SD) and Cmax and AUC values were 296 ± 90 ng/mL and 2287 ± 685 ng•hr/mL, respectively. The oral bioavailability of tenofovir from tenofovir DF in fasted subjects is approximately 25%. In vitro binding of tenofovir to human plasma proteins is <0.7% and is independent of concentration over the range of 0.01–25 μg/mL. Approximately 70–80% of the intravenous dose of tenofovir is recovered as unchanged drug in the urine. Tenofovir is eliminated by a combination of glomerular filtration and active tubular secretion with a renal clearance in adults with normal renal function of 243 ± 33 mL/min (mean ± SD). Following a single oral dose, the terminal elimination half-life of tenofovir is approximately 17 hours.

Effects of Food on Oral Absorption

ATRIPLA has not been evaluated in the presence of food. Administration of efavirenz tablets with a high fat meal increased the mean AUC and Cmax of efavirenz by 28% and 79%, respectively, compared to administration in the fasted state. Compared to fasted administration, dosing of tenofovir DF and emtricitabine in combination with either a high fat meal or a light meal increased the mean AUC and Cmax of tenofovir by 35% and 15%, respectively, without affecting emtricitabine exposures [See Dosage and Administration (2) and Patient Counseling Information (17.3)].

Special Populations

Race

Efavirenz: The pharmacokinetics of efavirenz in HIV-1 infected subjects appear to be similar among the racial groups studied.

Emtricitabine: No pharmacokinetic differences due to race have been identified following the administration of emtricitabine.

Tenofovir Disoproxil Fumarate: There were insufficient numbers from racial and ethnic groups other than Caucasian to adequately determine potential pharmacokinetic differences among these populations following the administration of tenofovir DF.

Gender

Efavirenz, Emtricitabine, and Tenofovir Disoproxil Fumarate: Efavirenz, emtricitabine, and tenofovir pharmacokinetics are similar in male and female subjects.

Pediatric and Geriatric Patients

Pharmacokinetic studies of tenofovir DF have not been performed in pediatric subjects (<18 years). Efavirenz has not been studied in pediatric subjects below 3 years of age or who weigh less than 13 kg. Emtricitabine has been studied in pediatric subjects from 3 months to 17 years of age. ATRIPLA is not recommended for pediatric administration. Pharmacokinetics of efavirenz, emtricitabine and tenofovir have not been fully evaluated in the elderly (>65 years) [See Use in Specific Populations (8)].

Patients with Impaired Renal Function

Efavirenz: The pharmacokinetics of efavirenz have not been studied in subjects with renal insufficiency; however, less than 1% of efavirenz is excreted unchanged in the urine, so the impact of renal impairment on efavirenz elimination should be minimal.

Emtricitabine and Tenofovir Disoproxil Fumarate: The pharmacokinetics of emtricitabine and tenofovir DF are altered in subjects with renal impairment. In subjects with creatinine clearance <50 mL/min, Cmax and AUC0–∞ of emtricitabine and tenofovir were increased [See Warnings and Precautions (5.7)].

Patients with Hepatic Impairment

Efavirenz: The pharmacokinetics of efavirenz have not been adequately studied in subjects with hepatic impairment [See Warnings and Precautions (5.10) and Use in Specific Populations (8.6)].

Emtricitabine: The pharmacokinetics of emtricitabine have not been studied in subjects with hepatic impairment; however, emtricitabine is not significantly metabolized by liver enzymes, so the impact of liver impairment should be limited.

Tenofovir Disoproxil Fumarate: The pharmacokinetics of tenofovir following a 300 mg dose of tenofovir DF have been studied in non-HIV infected subjects with moderate to severe hepatic impairment. There were no substantial alterations in tenofovir pharmacokinetics in subjects with hepatic impairment compared with unimpaired subjects.

Assessment of Drug Interactions

The drug interaction studies described were conducted with efavirenz, emtricitabine, or tenofovir DF as individual agents; no drug interaction studies have been conducted using ATRIPLA.

Efavirenz: The steady-state pharmacokinetics of efavirenz and tenofovir were unaffected when efavirenz and tenofovir DF were administered together versus each agent dosed alone. Specific drug interaction studies have not been performed with efavirenz and NRTIs other than tenofovir, lamivudine, and zidovudine. Clinically significant interactions would not be expected based on NRTIs elimination pathways.

Efavirenz has been shown in vivo to cause hepatic enzyme induction, thus increasing the biotransformation of some drugs metabolized by CYP3A. In vitro studies have shown that efavirenz inhibited CYP isozymes 2C9, 2C19, and 3A4 with Ki values (8.5–17 µM) in the range of observed efavirenz plasma concentrations. In in vitro studies, efavirenz did not inhibit CYP2E1 and inhibited CYP2D6 and CYP1A2 (Ki values 82–160 µM) only at concentrations well above those achieved clinically. Coadministration of efavirenz with drugs primarily metabolized by 2C9, 2C19, and 3A4 isozymes may result in altered plasma concentrations of the coadministered drug. Drugs which induce CYP3A activity would be expected to increase the clearance of efavirenz resulting in lowered plasma concentrations.

Drug interaction studies were performed with efavirenz and other drugs likely to be coadministered or drugs commonly used as probes for pharmacokinetic interaction. There was no clinically significant interaction observed between efavirenz and zidovudine, lamivudine, azithromycin, fluconazole, lorazepam, cetirizine, or paroxetine. Single doses of famotidine or an aluminum and magnesium antacid with simethicone had no effects on efavirenz exposures. The effects of coadministration of efavirenz on Cmax, AUC, and Cmin are summarized in Table 5 (effect of other drugs on efavirenz) and Table 6 (effect of efavirenz on other drugs). For information regarding clinical recommendations see Drug Interactions (7).

Table 5 Drug Interactions: Changes in Pharmacokinetic Parameters for Efavirenz in the Presence of the Coadministered Drug
 |  |  |  | Mean % Change of Efavirenz Pharmacokinetic Parameters [Increase = ↑; Decrease = ↓; No Effect = ↔] (90% CI)
Coadministered Drug | Dose of Coadministered Drug (mg) | Efavirenz Dose (mg) | N | Cmax | AUC | Cmin
Indinavir | 800 mg q8h × 14 days | 200 mg × 14 days | 11 | ↔ | ↔ | ↔
Lopinavir/ ritonavir | 400/100 mg q12h × 9 days | 600 mg × 9 days | 11, 12 [Parallel-group design; N for efavirenz + lopinavir/ritonavir, N for efavirenz alone.] | ↔ | ↓ 16 (↓ 38 to ↑ 15) | ↓ 16 (↓ 42 to ↑ 20)
Nelfinavir | 750 mg q8h × 7 days | 600 mg × 7 days | 10 | ↓ 12 (↓ 32 to ↑ 13) [95% CI] | ↓ 12 (↓ 35 to ↑ 18) | ↓ 21 (↓ 53 to ↑ 33)
Ritonavir | 500 mg q12h × 8 days | 600 mg × 10 days | 9 | ↑ 14 (↑ 4 to ↑ 26) | ↑ 21 (↑ 10 to ↑ 34) | ↑ 25 (↑ 7 to ↑ 46)
Saquinavir SGC [Soft Gelatin Capsule] | 1200 mg q8h × 10 days | 600 mg × 10 days | 13 | ↓ 13 (↓ 5 to ↓ 20) | ↓ 12 (↓ 4 to ↓ 19) | ↓ 14 (↓ 2 to ↓ 24)
Clarithromycin | 500 mg q12h × 7 days | 400 mg × 7 days | 12 | ↑ 11 (↑ 3 to ↑ 19) | ↔ | ↔
Itraconazole | 200 mg q12h × 14 days | 600 mg × 28 days | 16 | ↔ | ↔ | ↔
Rifabutin | 300 mg qd × 14 days | 600 mg × 14 days | 11 | ↔ | ↔ | ↓ 12 (↓ 24 to ↑ 1)
Rifampin | 600 mg × 7 days | 600 mg × 7 days | 12 | ↓ 20 (↓ 11 to ↓ 28) | ↓ 26 (↓ 15 to ↓ 36) | ↓ 32 (↓ 15 to ↓ 46)
Atorvastatin | 10 mg qd × 4 days | 600 mg × 15 days | 14 | ↔ | ↔ | ↔
Pravastatin | 40 mg qd × 4 days | 600 mg × 15 days | 11 | ↔ | ↔ | ↔
Simvastatin | 40 mg qd × 4 days | 600 mg × 15 days | 14 | ↓ 12 (↓ 28 to ↑ 8) | ↔ | ↓ 12 (↓ 25 to ↑ 3)
Carbamazepine | 200 mg qd × 3 days, 200 mg bid × 3 days, then 400 mg qd × 15 days | 600 mg × 35 days | 14 | ↓ 21 (↓ 15 to ↓ 26) | ↓ 36 (↓ 32 to ↓ 40) | ↓ 47 (↓ 41 to ↓ 53)
Diltiazem | 240 mg × 14 days | 600 mg × 28 days | 12 | ↑ 16 (↑ 6 to ↑ 26) | ↑ 11 (↑ 5 to ↑ 18) | ↑ 13 (↑ 1 to ↑ 26)
Sertraline | 50 mg qd × 14 days | 600 mg × 14 days | 13 | ↑ 11 (↑ 6 to ↑ 16) | ↔ | ↔
Voriconazole | 400 mg po q12h × 1 day then 200 mg po q12h × 8 days | 400 mg × 9 days | NA | ↑ 38 [90% CI not available] | ↑ 44 | NA
Voriconazole | 300 mg po q12h days 2–7 | 300 mg × 7 days | NA | ↓ 14 [Relative to steady-state administration of efavirenz (600 mg once daily for 9 days).] (↓ 7 to ↓ 21) | ↔ | NA
Voriconazole | 400 mg po q12h days 2–7 | 300 mg × 7 days | NA | ↔ | ↑ 17 (↑ 6 to ↑ 29) | NA
NA = not available

Table 6 Drug Interactions: Changes in Pharmacokinetic Parameters for Coadministered Drug in the Presence of Efavirenz
 |  |  |  | Mean % Change of Coadministered Drug Pharmacokinetic Parameters [Increase = ↑; Decrease = ↓; No Effect = ↔] (90% CI)
Coadministered Drug | Dose of Coadministered Drug (mg) | Efavirenz Dose (mg) | N | Cmax | AUC | Cmin
Atazanavir | 400 mg qd with a light meal d 1–20 | 600 mg qd with a light meal d 7–20 | 27 | ↓ 59 (↓ 49 to ↓ 67) | ↓ 74 (↓ 68 to ↓ 78) | ↓ 93 (↓ 90 to ↓ 95)
 | 400 mg qd d 1–6, then 300 mg qd d 7–20 with ritonavir 100 mg qd and a light meal | 600 mg qd 2 h after atazanavir and ritonavir d 7–20 | 13 | ↑ 14 [Compared with atazanavir 400 mg qd alone.] (↓ 17 to ↑ 58) | ↑ 39 (↑ 2 to ↑ 88) | ↑ 48 (↑ 24 to ↑ 76)
 | 300 mg qd/ritonavir 100 mg qd d 1–10 (pm), then 400 mg qd/ritonavir 100 mg qd d 11–24 (pm) (simultaneous with efavirenz) | 600 mg qd with a light snack d 11–24 (pm) | 14 | ↑ 17 (↑ 8 to ↑ 27) | ↔ | ↓ 42 (↓ 31 to ↓ 51)
Indinavir | 1000 mg q8h × 10 days | 600 mg × 10 days | 20
 | After morning dose |  |  | ↔ [Comparator dose of indinavir was 800 mg q8h × 10 days.] | ↓ 33 (↓ 26 to ↓ 39) | ↓ 39 (↓ 24 to ↓ 51)
 | After afternoon dose |  |  | ↔ | ↓ 37 (↓ 26 to ↓ 46) | ↓ 52 (↓ 47 to ↓ 57)
 | After evening dose |  |  | ↓ 29 (↓ 11 to ↓ 43) | ↓ 46 (↓ 37 to ↓ 54) | ↓ 57 (↓ 50 to ↓ 63)
Lopinavir/ ritonavir | 400/100 mg q12h × 9 days | 600 mg × 9 days | 11, 7 [Parallel-group design; N for efavirenz + lopinavir/ritonavir, N for lopinavir/ritonavir alone.] | ↔ [Values are for lopinavir. The pharmacokinetics of ritonavir 100 mg q12h are unaffected by concurrent efavirenz.] | ↓ 19 (↓ 36 to ↑ 3) | ↓ 39 (↓ 3 to ↓ 62)
Nelfinavir | 750 mg q8h × 7 days | 600 mg × 7 days | 10 | ↑ 21 (↑ 10 to ↑ 33) | ↑ 20 (↑ 8 to ↑ 34) | ↔
Metabolite AG-1402 |  |  |  | ↓ 40 (↓ 30 to ↓ 48) | ↓ 37 (↓ 25 to ↓ 48) | ↓ 43 (↓ 21 to ↓ 59)
Ritonavir | 500 mg q12h × 8 days | 600 mg × 10 days | 11
 | After AM dose |  |  | ↑ 24 (↑ 12 to ↑ 38) | ↑ 18 (↑ 6 to ↑ 33) | ↑ 42 (↑ 9 to ↑ 86)
 | After PM dose |  |  | ↔ | ↔ | ↑ 24 (↑ 3 to ↑ 50) [95% CI]
Saquinavir SGC [Soft Gelatin Capsule] | 1200 mg q8h × 10 days | 600 mg × 10 days | 12 | ↓ 50 (↓ 28 to ↓ 66) | ↓ 62 (↓ 45 to ↓ 74) | ↓ 56 (↓ 16 to ↓ 77)
Clarithromycin | 500 mg q12h × 7 days | 400 mg × 7 days | 11 | ↓ 26 (↓ 15 to ↓ 35) | ↓ 39 (↓ 30 to ↓ 46) | ↓ 53 (↓ 42 to ↓ 63)
14-OH metabolite |  |  |  | ↑ 49 (↑ 32 to ↑ 69) | ↑ 34 (↑ 18 to ↑ 53) | ↑ 26 (↑ 9 to ↑ 45)
Itraconazole | 200 mg q12h × 28 days | 600 mg ×14 days | 18 | ↓ 37 (↓ 20 to ↓ 51) | ↓ 39 (↓ 21 to ↓ 53) | ↓ 44 (↓ 27 to ↓ 58)
Hydroxy-itraconazole | 200 mg q12h × 28 days | 600 mg ×14 days | 18 | ↓ 35 (↓ 12 to ↓ 52) | ↓ 37 (↓ 14 to ↓ 55) | ↓ 43 (↓ 18 to ↓ 60)
Rifabutin | 300 mg qd × 14 days | 600 mg × 14 days | 9 | ↓ 32 (↓ 15 to ↓ 46) | ↓ 38 (↓ 28 to ↓ 47) | ↓ 45 (↓ 31 to ↓ 56)
Atorvastatin | 10 mg qd × 4 days | 600 mg × 15 days | 14 | ↓ 14 (↓ 1 to ↓ 26) | ↓ 43 (↓ 34 to ↓ 50) | ↓ 69 (↓ 49 to ↓ 81)
Total active (including metabolites) |  |  |  | ↓ 15 (↓ 2 to ↓ 26) | ↓ 32 (↓ 21 to ↓ 41) | ↓ 48 (↓ 23 to ↓ 64)
Pravastatin | 40 mg qd × 4 days | 600 mg × 15 days | 13 | ↓ 32 (↓ 59 to ↑ 12) | ↓ 44 (↓ 26 to ↓ 57) | ↓ 19 (↓ 0 to ↓ 35)
Simvastatin | 40 mg qd × 4 days | 600 mg × 15 days | 14 | ↓ 72 (↓ 63 to ↓ 79) | ↓ 68 (↓ 62 to ↓ 73) | ↓ 45 (↓ 20 to ↓ 62)
Total active (including metabolites) |  |  |  | ↓ 68 (↓ 55 to ↓ 78) | ↓ 60 (↓ 52 to ↓ 68) | NA [Not available because of insufficient data.]
Carbamazepine | 200 mg qd × 3 days, 200 mg bid × 3 days, then 400 mg qd × 29 days | 600 mg × 14 days | 12 | ↓ 20 (↓ 15 to ↓ 24) | ↓ 27 (↓ 20 to ↓ 33) | ↓ 35 (↓ 24 to ↓ 44)
Epoxide metabolite |  |  |  | ↔ | ↔ | ↓ 13 (↓ 30 to ↑ 7)
Diltiazem | 240 mg × 21 days | 600 mg × 14 days | 13 | ↓ 60 (↓ 50 to ↓ 68) | ↓ 69 (↓ 55 to ↓ 79) | ↓ 63 (↓ 44 to ↓ 75)
Desacetyl diltiazem | 240 mg × 21 days | 600 mg × 14 days | 13 | ↓ 64 (↓ 57 to ↓ 69) | ↓ 75 (↓ 59 to ↓ 84) | ↓ 62 (↓ 44 to ↓ 75)
N-monodesmethyl diltiazem | 240 mg × 21 days | 600 mg × 14 days | 13 | ↓ 28 (↓ 7 to ↓ 44) | ↓ 37 (↓ 17 to ↓ 52) | ↓ 37 (↓ 17 to ↓ 52)
Ethinyl estradiol/ Norgestimate | 0.035 mg/0.25 mg × 14 days | 600 mg × 14 days
Ethinyl estradiol | 0.035 mg/0.25 mg × 14 days | 600 mg × 14 days | 21 | ↔ | ↔ | ↔
Norelgestromin | 0.035 mg/0.25 mg × 14 days | 600 mg × 14 days | 21 | ↓ 46 (↓39 to ↓ 52) | ↓ 64 (↓ 62 to ↓ 67) | ↓ 82 (↓ 79 to ↓ 85)
Levonorgestrel | 0.035 mg/0.25 mg × 14 days | 600 mg × 14 days | 6 | ↓ 80 (↓77 to ↓ 83) | ↓ 83 (↓79 to ↓ 87) | ↓ 86 (↓80 to ↓ 90)
Methadone | Stable maintenance 35–100 mg daily | 600 mg × 14–21 days | 11 | ↓ 45 (↓ 25 to ↓ 59) | ↓ 52 (↓ 33 to ↓ 66) | NA
Sertraline | 50 mg qd × 14 days | 600 mg × 14 days | 13 | ↓ 29 (↓ 15 to ↓ 40) | ↓ 39 (↓ 27 to ↓ 50) | ↓ 46 (↓ 31 to ↓ 58)
Voriconazole | 400 mg po q12h × 1 day then 200 mg po q12h × 8 days | 400 mg × 9 days | NA | ↓ 61 [90% CI not available] | ↓ 77 | NA
Voriconazole | 300 mg po q12h days 2–7 | 300 mg × 7 days | NA | ↓ 36 [Relative to steady-state administration of voriconazole (400 mg for 1 day, then 200 mg po q12h for 2 days).] (↓ 21 to ↓ 49) | ↓ 55 (↓ 45 to ↓ 62) | NA
Voriconazole | 400 mg po q12h days 2–7 | 300 mg × 7 days | NA | ↑ 23 (↓ 1 to ↑ 53 | ↓ 7 (↓ 23 to ↑ 13) | NA
NA = not available

Emtricitabine and Tenofovir Disoproxil Fumarate: The steady-state pharmacokinetics of emtricitabine and tenofovir were unaffected when emtricitabine and tenofovir DF were administered together versus each agent dosed alone.

In vitro and clinical pharmacokinetic drug-drug interaction studies have shown that the potential for CYP mediated interactions involving emtricitabine and tenofovir with other medicinal products is low.

Emtricitabine and tenofovir are primarily excreted by the kidneys by a combination of glomerular filtration and active tubular secretion. No drug-drug interactions due to competition for renal excretion have been observed; however, coadministration of emtricitabine and tenofovir DF with drugs that are eliminated by active tubular secretion may increase concentrations of emtricitabine, tenofovir, and/or the coadministered drug.

Drugs that decrease renal function may increase concentrations of emtricitabine and/or tenofovir.

No clinically significant drug interactions have been observed between emtricitabine and famciclovir, indinavir, stavudine, tenofovir DF and zidovudine. Similarly, no clinically significant drug interactions have been observed between tenofovir DF and abacavir, efavirenz, emtricitabine, entecavir, indinavir, lamivudine, lopinavir/ritonavir, methadone, nelfinavir, oral contraceptives, ribavirin, saquinavir/ritonavir or tacrolimus in studies conducted in healthy volunteers.

Following multiple dosing to HIV-negative subjects receiving either chronic methadone maintenance therapy, oral contraceptives, or single doses of ribavirin, steady-state tenofovir pharmacokinetics were similar to those observed in previous studies, indicating a lack of clinically significant drug interactions between these agents and tenofovir DF.

The effects of coadministered drugs on the Cmax, AUC, and Cmin of tenofovir are shown in Table 7. The effects of coadministration of tenofovir DF on Cmax, AUC, and Cmin of coadministered drugs are shown in Table 8 and Table 9.

Table 7 Drug Interactions: Changes in Pharmacokinetic Parameters for Tenofovir in the Presence of the Coadministered Drug [All interaction studies conducted in healthy volunteers.] , [Subjects received tenofovir DF 300 mg once daily.]
Coadministered Drug | Dose of Coadministered Drug (mg) | N | Mean % Change of Tenofovir Pharmacokinetic Parameters [Increase = ↑; Decrease = ↓; No Effect = ↔] (90% CI)
Coadministered Drug | Dose of Coadministered Drug (mg) | N | Cmax | AUC | Cmin
Atazanavir [Reyataz Prescribing Information] | 400 once daily × 14 days | 33 | ↑ 14 (↑ 8 to ↑ 20) | ↑ 24 (↑ 21 to ↑ 28) | ↑ 22 (↑ 15 to ↑ 30)
Didanosine (enteric-coated) | 400 once | 25 | ↔ | ↔ | ↔
Didanosine (buffered) | 250 or 400 once daily × 7 days | 14 | ↔ | ↔ | ↔
Lopinavir/ ritonavir | 400/100 twice daily × 14 days | 24 | ↔ | ↑ 32 (↑ 25 to ↑ 38) | ↑ 51 (↑ 37 to ↑ 66)

Table 8 Drug Interactions: Changes in Pharmacokinetic Parameters for Coadministered Drug in the Presence of Tenofovir Disoproxil Fumarate [All interaction studies conducted in healthy volunteers.] , [Subjects received tenofovir DF 300 mg once daily.]
Coadministered Drug | Dose of Coadministered Drug (mg) | N | Mean % Change of Coadministered Drug Pharmacokinetic Parameters [Increase = ↑; Decrease = ↓; No Effect = ↔] (90% CI)
Coadministered Drug | Dose of Coadministered Drug (mg) | N | Cmax | AUC | Cmin
Atazanavir [Reyataz Prescribing Information] | 400 once daily × 14 days | 34 | ↓ 21 (↓ 27 to ↓ 14) | ↓ 25 (↓ 30 to ↓ 19) | ↓ 40 (↓ 48 to ↓ 32)
 | Atazanavir/ritonavir 300/100 once daily × 42 days | 10 | ↓ 28 (↓ 50 to ↑ 5) | ↓ 25 [In HIV-infected patients, addition of tenofovir DF to atazanavir 300 mg plus ritonavir 100 mg, resulted in AUC and Cmin values of atazanavir that were 2.3- and 4-fold higher than the respective values observed for atazanavir 400 mg when given alone.] (↓ 42 to ↓ 3) | ↓ 23 (↓ 46 to ↑ 10)
Lopinavir | Lopinavir/ritonavir 400/100 twice daily × 14 days | 24 | ↔ | ↔ | ↔
Ritonavir | Lopinavir/ritonavir 400/100 twice daily × 14 days | 24 | ↔ | ↔ | ↔

Coadministration of tenofovir DF with didanosine results in changes in the pharmacokinetics of didanosine that may be of clinical significance. Table 9 summarizes the effects of tenofovir DF on the pharmacokinetics of didanosine. Concomitant dosing of tenofovir DF with didanosine buffered tablets or enteric-coated capsules significantly increases the Cmax and AUC of didanosine. When didanosine 250 mg enteric-coated capsules were administered with tenofovir DF, systemic exposures of didanosine were similar to those seen with the 400 mg enteric-coated capsules alone under fasted conditions. The mechanism of this interaction is unknown [for didanosine dosing adjustment recommendations see Drug Interactions (7.3), Table 4].

Table 9 Drug Interactions: Changes in Pharmacokinetic Parameters for Didanosine in the Presence of Tenofovir Disoproxil Fumarate [All interaction studies conducted in healthy volunteers.] , [Subjects received tenofovir DF 300 mg once daily.]
Didanosine Dose (mg)/Method of Administration [Administration with food was with a light meal (~373 kcal, 20% fat).] | Tenofovir DF Method of Administration, | N | Mean % Change (90% CI) vs. Didanosine 400 mg Alone, Fasted [Increase = ↑; Decrease = ↓; No Effect = ↔]
Didanosine Dose (mg)/Method of Administration [Administration with food was with a light meal (~373 kcal, 20% fat).] | Tenofovir DF Method of Administration, | N | Cmax | AUC
Buffered tablets
400 once daily [Includes 4 subjects weighing <60 kg receiving ddI 250 mg.] × 7 days | Fasted 1 hour after didanosine | 14 | ↑ 28 (↑ 11 to ↑ 48) | ↑ 44 (↑ 31 to ↑ 59)
Enteric coated capsules
400 once, fasted | With food, 2 hr after didanosine | 26 | ↑ 48 (↑ 25 to ↑ 76) | ↑ 48 (↑ 31 to ↑ 67)
400 once, with food | Simultaneously with didanosine | 26 | ↑ 64 (↑ 41 to ↑ 89) | ↑ 60 (↑ 44 to ↑ 79)
250 once, fasted | With food, 2 hr after didanosine | 28 | ↓ 10 (↓ 22 to ↑ 3) | ↔
250 once, fasted | Simultaneously with didanosine | 28 | ↔ | ↑ 14 (0 to ↑ 31)
250 once, with food | Simultaneously with didanosine | 28 | ↓ 29 (↓ 39 to ↓ 18) | ↓ 11 (↓ 23 to ↑ 2)

Mechanism of Action

Efavirenz: Efavirenz is a non-nucleoside reverse transcriptase (RT) inhibitor of HIV-1. Efavirenz activity is mediated predominantly by noncompetitive inhibition of HIV-1 reverse transcriptase (RT). HIV-2 RT and human cellular DNA polymerases α, β, γ, and δ are not inhibited by efavirenz.

Emtricitabine: Emtricitabine, a synthetic nucleoside analog of cytidine, is phosphorylated by cellular enzymes to form emtricitabine 5'-triphosphate. Emtricitabine 5'-triphosphate inhibits the activity of the HIV-1 RT by competing with the natural substrate deoxycytidine 5'-triphosphate and by being incorporated into nascent viral DNA which results in chain termination. Emtricitabine 5'-triphosphate is a weak inhibitor of mammalian DNA polymerase α, β, ε, and mitochondrial DNA polymerase γ.

Tenofovir Disoproxil Fumarate: Tenofovir DF is an acyclic nucleoside phosphonate diester analog of adenosine monophosphate. Tenofovir DF requires initial diester hydrolysis for conversion to tenofovir and subsequent phosphorylations by cellular enzymes to form tenofovir diphosphate. Tenofovir diphosphate inhibits the activity of HIV-1 RT by competing with the natural substrate deoxyadenosine 5'-triphosphate and, after incorporation into DNA, by DNA chain termination. Tenofovir diphosphate is a weak inhibitor of mammalian DNA polymerases α, β, and mitochondrial DNA polymerase γ.

Antiviral Activity

Efavirenz, Emtricitabine, and Tenofovir Disoproxil Fumarate: In combination studies evaluating the antiviral activity in cell culture of emtricitabine and efavirenz together, efavirenz and tenofovir together, and emtricitabine and tenofovir together, additive to synergistic antiviral effects were observed.

Efavirenz: The concentration of efavirenz inhibiting replication of wild-type laboratory adapted strains and clinical isolates in cell culture by 90–95% (EC90–95) ranged from 1.7–25 nM in lymphoblastoid cell lines, peripheral blood mononuclear cells, and macrophage/monocyte cultures. Efavirenz demonstrated additive antiviral activity against HIV-1 in cell culture when combined with non-nucleoside reverse transcriptase inhibitors (NNRTIs) (delavirdine and nevirapine), nucleoside reverse transcriptase inhibitors (NRTIs) (abacavir, didanosine, lamivudine, stavudine, zalcitabine, and zidovudine), protease inhibitors (PIs) (amprenavir, indinavir, lopinavir, nelfinavir, ritonavir, and saquinavir), and the fusion inhibitor enfuvirtide. Efavirenz demonstrated additive to antagonistic antiviral activity in cell culture with atazanavir. Efavirenz demonstrated antiviral activity against clade B and most non-clade B isolates (subtypes A, AE, AG, C, D, F, G, J, and N), but had reduced antiviral activity against group O viruses. Efavirenz is not active against HIV-2.

Emtricitabine: The antiviral activity in cell culture of emtricitabine against laboratory and clinical isolates of HIV-1 was assessed in lymphoblastoid cell lines, the MAGI-CCR5 cell line, and peripheral blood mononuclear cells. The 50% effective concentration (EC50) values for emtricitabine were in the range of 0.0013–0.64 µM (0.0003–0.158 µg/mL). In drug combination studies of emtricitabine with NRTIs (abacavir, lamivudine, stavudine, zalcitabine, and zidovudine), NNRTIs (delavirdine, efavirenz, and nevirapine), and PIs (amprenavir, nelfinavir, ritonavir, and saquinavir), additive to synergistic effects were observed. Emtricitabine displayed antiviral activity in cell culture against HIV-1 clades A, B, C, D, E, F, and G (EC50 values ranged from 0.007–0.075 µM) and showed strain specific activity against HIV-2 (EC50 values ranged from 0.007–1.5 µM).

Tenofovir Disoproxil Fumarate: The antiviral activity in cell culture of tenofovir against laboratory and clinical isolates of HIV-1 was assessed in lymphoblastoid cell lines, primary monocyte/macrophage cells and peripheral blood lymphocytes. The EC50 values for tenofovir were in the range of 0.04–8.5 µM. In drug combination studies of tenofovir with NRTIs (abacavir, didanosine, lamivudine, stavudine, zalcitabine, and zidovudine), NNRTIs (delavirdine, efavirenz, and nevirapine), and PIs (amprenavir, indinavir, nelfinavir, ritonavir, and saquinavir), additive to synergistic effects were observed. Tenofovir displayed antiviral activity in cell culture against HIV-1 clades A, B, C, D, E, F, G and O (EC50 values ranged from 0.5–2.2 µM) and showed strain specific activity against HIV-2 (EC50 values ranged from 1.6 µM to 5.5 µM).

Resistance

Efavirenz, Emtricitabine, and Tenofovir Disoproxil Fumarate: HIV-1 isolates with reduced susceptibility to the combination of emtricitabine and tenofovir have been selected in cell culture and in clinical studies. Genotypic analysis of these isolates identified the M184V/I and/or K65R amino acid substitutions in the viral RT.

In a clinical study of treatment-naive subjects [Study 934, see Clinical Studies (14)] resistance analysis was performed on HIV-1 isolates from all confirmed virologic failure subjects with >400 copies/mL of HIV-1 RNA at Week 144 or early discontinuations. Genotypic resistance to efavirenz, predominantly the K103N substitution, was the most common form of resistance that developed. Resistance to efavirenz occurred in 13/19 analyzed subjects in the emtricitabine + tenofovir DF group and in 21/29 analyzed subjects in the zidovudine/lamivudine fixed-dose combination group. The M184V amino acid substitution, associated with resistance to emtricitabine and lamivudine, was observed in 2/19 analyzed subject isolates in the emtricitabine + tenofovir DF group and in 10/29 analyzed subject isolates in the zidovudine/lamivudine group. Through 144 weeks of Study 934, no subjects developed a detectable K65R substitution in their HIV-1 as analyzed through standard genotypic analysis.

In a clinical study of treatment-naive subjects, isolates from 8/47 (17%) analyzed subjects receiving tenofovir DF developed the K65R substitution through 144 weeks of therapy; 7 of these occurred in the first 48 weeks of treatment and one at Week 96. In treatment experienced subjects, 14/304 (5%) of tenofovir DF treated subjects with virologic failure through Week 96 showed >1.4 fold (median 2.7) reduced susceptibility to tenofovir. Genotypic analysis of the resistant isolates showed a substitution in the HIV-1 RT gene resulting in the K65R amino acid substitution.

Efavirenz: Clinical isolates with reduced susceptibility in cell culture to efavirenz have been obtained. The most frequently observed amino acid substitution in clinical studies with efavirenz is K103N (54%). One or more RT substitutions at amino acid positions 98, 100, 101, 103, 106, 108, 188, 190, 225, 227, and 230 were observed in subjects failing treatment with efavirenz in combination with other antiretrovirals. Other resistance substitutions observed to emerge commonly included L100I (7%), K101E/Q/R (14%), V108I (11%), G190S/T/A (7%), P225H (18%), and M230I/L (11%).

HIV-1 isolates with reduced susceptibility to efavirenz (>380-fold increase in EC90 value) emerged rapidly under selection in cell culture. Genotypic characterization of these viruses identified substitutions resulting in single amino acid substitutions L100I or V179D, double substitutions L100I/V108I, and triple substitutions L100I/V179D/Y181C in RT.

Emtricitabine: Emtricitabine-resistant isolates of HIV-1 have been selected in cell culture and in clinical studies. Genotypic analysis of these isolates showed that the reduced susceptibility to emtricitabine was associated with a substitution in the HIV-1 RT gene at codon 184 which resulted in an amino acid substitution of methionine by valine or isoleucine (M184V/I).

Tenofovir Disoproxil Fumarate: HIV-1 isolates with reduced susceptibility to tenofovir have been selected in cell culture. These viruses expressed a K65R substitution in RT and showed a 2–4 fold reduction in susceptibility to tenofovir.

Cross Resistance

Efavirenz, Emtricitabine, and Tenofovir Disoproxil Fumarate: Cross-resistance has been recognized among NNRTIs. Cross resistance has also been recognized among certain NRTIs. The M184V/I and/or K65R substitutions selected in cell culture by the combination of emtricitabine and tenofovir are also observed in some HIV-1 isolates from subjects failing treatment with tenofovir in combination with either lamivudine or emtricitabine, and either abacavir or didanosine. Therefore, cross-resistance among these drugs may occur in patients whose virus harbors either or both of these amino acid substitutions.

Efavirenz: Clinical isolates previously characterized as efavirenz-resistant were also phenotypically resistant in cell culture to delavirdine and nevirapine compared to baseline. Delavirdine- and/or nevirapine-resistant clinical viral isolates with NNRTI resistance-associated substitutions (A98G, L100I, K101E/P, K103N/S, V106A, Y181X, Y188X, G190X, P225H, F227L, or M230L) showed reduced susceptibility to efavirenz in cell culture. Greater than 90% of NRTI-resistant isolates tested in cell culture retained susceptibility to efavirenz.

Emtricitabine: Emtricitabine-resistant isolates (M184V/I) were cross-resistant to lamivudine and zalcitabine but retained susceptibility in cell culture to didanosine, stavudine, tenofovir, zidovudine, and NNRTIs (delavirdine, efavirenz, and nevirapine). HIV-1 isolates containing the K65R substitution, selected in vivo by abacavir, didanosine, tenofovir, and zalcitabine, demonstrated reduced susceptibility to inhibition by emtricitabine. Viruses harboring substitutions conferring reduced susceptibility to stavudine and zidovudine (M41L, D67N, K70R, L210W, T215Y/F, and K219Q/E) or didanosine (L74V) remained sensitive to emtricitabine.

Tenofovir Disoproxil Fumarate: The K65R substitution selected by tenofovir is also selected in some HIV-1 infected patients treated with abacavir, didanosine, or zalcitabine. HIV-1 isolates with the K65R substitution also showed reduced susceptibility to emtricitabine and lamivudine. Therefore, cross-resistance among these drugs may occur in patients whose virus harbors the K65R substitution. HIV-1 isolates from patients (N=20) whose HIV-1 expressed a mean of 3 zidovudine-associated RT amino acid substitutions (M41L, D67N, K70R, L210W, T215Y/F, or K219Q/E/N) showed a 3.1-fold decrease in the susceptibility to tenofovir. Subjects whose virus expressed an L74V substitution without zidovudine resistance associated substitutions (N=8) had reduced response to VIREAD. Limited data are available for patients whose virus expressed a Y115F substitution (N=3), Q151M substitution (N=2), or T69 insertion (N=4), all of whom had a reduced response.

13 NONCLINICAL TOXICOLOGY

Efavirenz: Long-term carcinogenicity studies in mice and rats were carried out with efavirenz. Mice were dosed with 0, 25, 75, 150, or 300 mg/kg/day for 2 years. Incidences of hepatocellular adenomas and carcinomas and pulmonary alveolar/bronchiolar adenomas were increased above background in females. No increases in tumor incidence above background were seen in males. In studies in which rats were administered efavirenz at doses of 0, 25, 50, or 100 mg/kg/day for 2 years, no increases in tumor incidence above background were observed. The systemic exposure (based on AUCs) in mice was approximately 1.7-fold that in humans receiving the 600-mg/day dose. The exposure in rats was lower than that in humans. The mechanism of the carcinogenic potential is unknown. However, in genetic toxicology assays, efavirenz showed no evidence of mutagenic or clastogenic activity in a battery of in vitro and in vivo studies. These included bacterial mutation assays in S. typhimurium and E. coli, mammalian mutation assays in Chinese hamster ovary cells, chromosome aberration assays in human peripheral blood lymphocytes or Chinese hamster ovary cells, and an in vivo mouse bone marrow micronucleus assay. Given the lack of genotoxic activity of efavirenz, the relevance to humans of neoplasms in efavirenz-treated mice is not known.

Efavirenz did not impair mating or fertility of male or female rats, and did not affect sperm of treated male rats. The reproductive performance of offspring born to female rats given efavirenz was not affected. As a result of the rapid clearance of efavirenz in rats, systemic drug exposures achieved in these studies were equivalent to or below those achieved in humans given therapeutic doses of efavirenz.

Emtricitabine: In long-term carcinogenicity studies of emtricitabine, no drug-related increases in tumor incidence were found in mice at doses up to 750 mg/kg/day (26 times the human systemic exposure at the therapeutic dose of 200 mg/day) or in rats at doses up to 600 mg/day (31 times the human systemic exposure at the therapeutic dose).

Emtricitabine was not genotoxic in the reverse mutation bacterial test (Ames test), mouse lymphoma or mouse micronucleus assays.

Emtricitabine did not affect fertility in male rats at approximately 140-fold or in male and female mice at approximately 60-fold higher exposures (AUC) than in humans given the recommended 200 mg daily dose. Fertility was normal in the offspring of mice exposed daily from before birth (in utero) through sexual maturity at daily exposures (AUC) of approximately 60-fold higher than human exposures at the recommended 200 mg daily dose.

Tenofovir Disoproxil Fumarate: Long-term oral carcinogenicity studies of tenofovir DF in mice and rats were carried out at exposures up to approximately 16 times (mice) and 5 times (rats) those observed in humans at the therapeutic dose for HIV-1 infection. At the high dose in female mice, liver adenomas were increased at exposures 16 times that in humans. In rats, the study was negative for carcinogenic findings at exposures up to 5 times that observed in humans at the therapeutic dose.

Tenofovir DF was mutagenic in the in vitro mouse lymphoma assay and negative in an in vitro bacterial mutagenicity test (Ames test). In an in vivo mouse micronucleus assay, tenofovir DF was negative when administered to male mice.

There were no effects on fertility, mating performance or early embryonic development when tenofovir DF was administered to male rats at a dose equivalent to 10 times the human dose based on body surface area comparisons for 28 days prior to mating and to female rats for 15 days prior to mating through day seven of gestation. There was, however, an alteration of the estrous cycle in female rats.

Efavirenz: Nonsustained convulsions were observed in 6 of 20 monkeys receiving efavirenz at doses yielding plasma AUC values 4- to 13-fold greater than those in humans given the recommended dose.

Tenofovir Disoproxil Fumarate: Tenofovir and tenofovir DF administered in toxicology studies to rats, dogs and monkeys at exposures (based on AUCs) greater than or equal to 6-fold those observed in humans caused bone toxicity. In monkeys the bone toxicity was diagnosed as osteomalacia. Osteomalacia observed in monkeys appeared to be reversible upon dose reduction or discontinuation of tenofovir. In rats and dogs, the bone toxicity manifested as reduced bone mineral density. The mechanism(s) underlying bone toxicity is unknown.

Evidence of renal toxicity was noted in 4 animal species administered tenofovir and tenofovir DF. Increases in serum creatinine, BUN, glycosuria, proteinuria, phosphaturia and/or calciuria and decreases in serum phosphate were observed to varying degrees in these animals. These toxicities were noted at exposures (based on AUCs) 2–20 times higher than those observed in humans. The relationship of the renal abnormalities, particularly the phosphaturia, to the bone toxicity is not known.

14 CLINICAL STUDIES

Clinical Study 934 supports the use of ATRIPLA tablets in antiretroviral treatment-naïve HIV-1 infected patients. Additional data in support of the use of ATRIPLA in treatment- naive patients can be found in the prescribing information for VIREAD.

Clinical Study 073 provides clinical experience in subjects with stable, virologic suppression and no history of virologic failure who switched from their current regimen to ATRIPLA.

In antiretroviral treatment-experienced patients, the use of ATRIPLA tablets may be considered for patients with HIV-1 strains that are expected to be susceptible to the components of ATRIPLA as assessed by treatment history or by genotypic or phenotypic testing [See Clinical Pharmacology (12.4)].

Study 934: Data through 144 weeks are reported for Study 934, a randomized, open-label, active-controlled multicenter study comparing emtricitabine + tenofovir DF administered in combination with efavirenz versus zidovudine/lamivudine fixed-dose combination administered in combination with efavirenz in 511 antiretroviral-naive subjects. From weeks 96 to 144 of the study, subjects received emtricitabine/tenofovir DF fixed-dose combination with efavirenz in place of emtricitabine + tenofovir DF with efavirenz. Subjects had a mean age of 38 years (range 18–80), 86% were male, 59% were Caucasian and 23% were Black. The mean baseline CD4^+ cell count was 245 cells/mm^3 (range 2–1191) and median baseline plasma HIV-1 RNA was 5.01 log10 copies/mL (range 3.56–6.54). Subjects were stratified by baseline CD4^+ cell count (< or ≥ 200 cells/mm^3) and 41% had CD4^+ cell counts <200 cells/mm^3. Fifty-one percent (51%) of subjects had baseline viral loads >100,000 copies/mL. Treatment outcomes through 48 and 144 weeks for those subjects who did not have efavirenz resistance at baseline (n=487) are presented in Table 10.

Table 10 Outcomes of Randomized Treatment at Weeks 48 and 144 (Study 934)
Outcomes | At Week 48 |  | At Week 144
Outcomes | FTC + TDF +EFV (N=244) | AZT/3TC +EFV (N=243) | FTC + TDF +EFV (N=227) [Subjects who were responders at Week 48 or Week 96 (HIV-1 RNA <400 copies/mL) but did not consent to continue study after Week 48 or Week 96 were excluded from analysis.] | AZT/3TC +EFV (N=229)
Responder [Subjects achieved and maintained confirmed HIV-1 RNA <400 copies/mL through Weeks 48 and 144.] | 84% | 73% | 71% | 58%
Virologic failure [Includes confirmed viral rebound and failure to achieve confirmed HIV-1 RNA <400 copies/mL through Weeks 48 and 144.] | 2% | 4% | 3% | 6%
Rebound | 1% | 3% | 2% | 5%
Never suppressed | 0% | 0% | 0% | 0%
Change in antiretroviral regimen | 1% | 1% | 1% | 1%
Death | <1% | 1% | 1% | 1%
Discontinued due to adverse event | 4% | 9% | 5% | 12%
Discontinued for other reasons [Includes lost to follow-up, patient withdrawal, noncompliance, protocol violation and other reasons.] | 10% | 14% | 20% | 22%

Through Week 48, 84% and 73% of subjects in the emtricitabine + tenofovir DF group and the zidovudine/lamivudine group, respectively, achieved and maintained HIV-1 RNA <400 copies/mL (71% and 58% through Week 144). The difference in the proportion of subjects who achieved and maintained HIV-1 RNA <400 copies/mL through 48 weeks largely results from the higher number of discontinuations due to adverse events and other reasons in the zidovudine/lamivudine group in this open-label study. In addition, 80% and 70% of subjects in the emtricitabine + tenofovir DF group and the zidovudine/lamivudine group, respectively, achieved and maintained HIV-1 RNA <50 copies/mL through Week 48 (64% and 56% through Week 144). The mean increase from baseline in CD4^+ cell count was 190 cells/mm^3 in the emtricitabine + tenofovir DF group and 158 cells/mm^3 in the zidovudine/lamivudine group at Week 48 (312 and 271 cells/mm^3 at Week 144).

Through 48 weeks, 7 subjects in the emtricitabine + tenofovir DF group and 5 subjects in the zidovudine/lamivudine group experienced a new CDC Class C event (10 and 6 subjects through 144 weeks).

Study 073: Study 073 was a 48-week open-label, randomized clinical trial in subjects with stable, virologic suppression on combination antiretroviral therapy consisting of at least two nucleoside reverse transcriptase inhibitors (NRTIs) administered in combination with a protease inhibitor (with or without ritonavir) or a non-nucleoside reverse transcriptase inhibitor (NNRTI).

To be enrolled, subjects were to have HIV-1 RNA <200 copies/mL for at least 12 weeks on their current regimen prior to study entry with no known HIV-1 substitutions conferring resistance to the components of ATRIPLA and no history of virologic failure.

The study compared the efficacy of switching to ATRIPLA or staying on the baseline antiretroviral regimen (SBR). Subjects were randomized in a 2:1 ratio to switch to ATRIPLA (N=203) or stay on SBR (N=97). Subjects had a mean age of 43 years (range 22 to 73 years), 88% were male, 68% were white, 29% were black or African-American, and 3% were of other races. At baseline, median CD4^+ cell count was 516 cells/mm^3 and 96% had HIV-1 RNA <50 copies/mL. The median time since onset of antiretroviral therapy was 3 years and 88% of subjects were receiving their first antiretroviral regimen at study enrollment.

At Week 48, 89% and 87% of subjects who switched to ATRIPLA maintained HIV RNA <200 copies/mL and <50 copies/mL, respectively, compared to 88% and 85% who remained on SBR; this difference was not statistically significant. No changes in CD4+ cell counts from baseline to Week 48 were observed in either treatment arm.

16 HOW SUPPLIED/STORAGE AND HANDLING

ATRIPLA tablets are pink, capsule-shaped, film-coated, debossed with "123" on one side and plain-faced on the other side.

They are supplied by State of Florida DOH Central Pharmacy as follows:

NDC | Strength | Quantity/Form | Color | Source NDC
53808-0208-1 | 600 mg / 200 mg / 300 mg | 30 TABLET | PINK | 15584-0101-1

STORAGE AND HANDLING

Store at 25 °C (77 °F); excursions permitted to 15–30 °C (59–86 °F) [see USP Controlled Room Temperature].

- Keep container tightly closed.
- Dispense only in original container.
- Do not use if seal over bottle opening is broken or missing.

17 PATIENT COUNSELING INFORMATION and FDA-APPROVED PATIENT LABELING

17.1 Drug Interactions

A statement to patients and healthcare providers is included on the product's bottle labels: ALERT: Find out about medicines that should NOT be taken with ATRIPLA. ATRIPLA may interact with some drugs; therefore, patients should be advised to report to their doctor the use of any other prescription, nonprescription medication, or herbal products, particularly St. John's wort.

17.2 Information for Patients

Patients should be advised that:

- ATRIPLA is not a cure for HIV-1 infection and that they may continue to experience illnesses associated with HIV-1 infection, including opportunistic infections. Patients should remain under the care of a physician when using ATRIPLA.
- The use of ATRIPLA has not been shown to reduce the risk of transmission of HIV-1 to others through sexual contact or blood contamination. Patients should be advised to continue to practice safer sex and to use latex or polyurethane condoms to lower the chance of sexual contact with any body fluids such as semen, vaginal secretions or blood. Patients should be advised never to re-use or share needles.
- The long term effects of ATRIPLA are unknown.
- Redistribution or accumulation of body fat may occur in patients receiving antiretroviral therapy and that the cause and long-term health effects of these conditions are not known.
- ATRIPLA should not be coadministered with SUSTIVA, EMTRIVA, VIREAD, or TRUVADA, or drugs containing lamivudine, including Combivir, Epivir, Epivir-HBV, Epzicom, or Trizivir.
- ATRIPLA should not be administered with HEPSERA [See Warnings and Precautions (5.2)].

17.3 Lactic Acidosis/Severe Hepatomegaly with Steatosis

Patients should be informed that lactic acidosis and severe hepatomegaly with steatosis, including fatal cases, have been reported. Treatment will be suspended in any patients who develop clinical symptoms suggestive of lactic acidosis or pronounced hepatotoxicity (including nausea, vomiting, unusual or unexpected stomach discomfort, and weakness) [See Warnings and Precautions (5.1)].

17.4 Patients Coinfected with HIV-1 and HBV

Patients with HIV-1 should be tested for hepatitis B virus (HBV) before initiating antiretroviral therapy.

Patients should be advised that severe acute exacerbations of hepatitis B have been reported in patients who are coinfected with HBV and HIV-1 and have discontinued EMTRIVA (emtricitabine) or VIREAD (tenofovir DF), which are components of ATRIPLA.

17.5 New Onset or Worsening Renal Impairment

Renal impairment, including cases of acute renal failure and Fanconi syndrome, has been reported. ATRIPLA should be avoided with concurrent or recent use of a nephrotoxic agent [See Warnings and Precautions (5.7)].

17.6 Decreases in Bone Mineral Density

Patients should be informed that decreases in bone mineral density have been observed with the use of tenofovir DF. Bone mineral density monitoring may be performed in patients who have a history of pathologic bone fracture or are at risk for osteopenia [See Warnings and Precautions (5.11)].

17.7 Dosing Instructions

Patients should be advised to take ATRIPLA orally on an empty stomach and that it is important to take ATRIPLA on a regular dosing schedule to avoid missing doses.

17.8 Nervous System Symptoms

Patients should be informed that central nervous system symptoms (NSS) including dizziness, insomnia, impaired concentration, drowsiness, and abnormal dreams are commonly reported during the first weeks of therapy with efavirenz. Dosing at bedtime may improve the tolerability of these symptoms, which are likely to improve with continued therapy. Patients should be alerted to the potential for additive effects when ATRIPLA is used concomitantly with alcohol or psychoactive drugs. Patients should be instructed that if they experience NSS they should avoid potentially hazardous tasks such as driving or operating machinery [See Warnings and Precautions (5.6), and Dosage and Administration (2)].

17.9 Psychiatric Symptoms

Patients should be informed that serious psychiatric symptoms including severe depression, suicide attempts, aggressive behavior, delusions, paranoia, and psychosis-like symptoms have been reported in patients receiving efavirenz. If they experience severe psychiatric adverse experiences they should seek immediate medical evaluation. Patients should be advised to inform their physician of any history of mental illness or substance abuse [See Warnings and Precautions (5.5)].

17.10 Rash

Patients should be informed that a common side effect is rash. Rashes usually go away without any change in treatment. However, since rash may be serious, patients should be advised to contact their physician promptly if rash occurs.

17.11 Reproductive Risk Potential

Women receiving ATRIPLA should be instructed to avoid pregnancy [See Warnings and Precautions (5.8)]. A reliable form of barrier contraception must always be used in combination with other methods of contraception, including oral or other hormonal contraception. Because of the long half-life of efavirenz, use of adequate contraceptive measures for 12 weeks after discontinuation of ATRIPLA is recommended. Women should be advised to notify their physician if they become pregnant or plan to become pregnant while taking ATRIPLA. If this drug is used during the first trimester of pregnancy, or if the patient becomes pregnant while taking this drug, she should be apprised of the potential harm to the fetus.

FDA-Approved Patient Labeling

Patient Information

ATRIPLA® (uh TRIP luh) Tablets

ALERT: Find out about medicines that should NOT be taken with ATRIPLA.

Please also read the section "MEDICINES YOU SHOULD NOT TAKE WITH ATRIPLA."

Generic name: efavirenz, emtricitabine and tenofovir disoproxil fumarate
(eh FAH vih renz, em tri SIT uh bean and te NOE' fo veer dye soe PROX il FYOU mar ate)

Read the Patient Information that comes with ATRIPLA before you start taking it and each time you get a refill since there may be new information. This information does not take the place of talking to your healthcare provider about your medical condition or treatment. You should stay under a healthcare provider's care when taking ATRIPLA. Do not change or stop your medicine without first talking with your healthcare provider. Talk to your healthcare provider or pharmacist if you have any questions about ATRIPLA.

What is the most important information I should know about ATRIPLA?

- Some people who have taken medicine like ATRIPLA (which contains nucleoside analogs) have developed a serious condition called lactic acidosis (build up of an acid in the blood). Lactic acidosis can be a medical emergency and may need to be treated in the hospital. Call your healthcare provider right away if you get the following signs or symptoms of lactic acidosis:
  - You feel very weak or tired.
  - You have unusual (not normal) muscle pain.
  - You have trouble breathing.
  - You have stomach pain with nausea and vomiting.
  - You feel cold, especially in your arms and legs.
  - You feel dizzy or lightheaded.
  - You have a fast or irregular heartbeat.
- Some people who have taken medicines like ATRIPLA have developed serious liver problems called hepatotoxicity, with liver enlargement (hepatomegaly) and fat in the liver (steatosis). Call your healthcare provider right away if you get the following signs or symptoms of liver problems:
  - Your skin or the white part of your eyes turns yellow (jaundice).
  - Your urine turns dark.
  - Your bowel movements (stools) turn light in color.
  - You don't feel like eating food for several days or longer.
  - You feel sick to your stomach (nausea).
  - You have lower stomach area (abdominal) pain.
- You may be more likely to get lactic acidosis or liver problems if you are female, very overweight (obese), or have been taking nucleoside analog-containing medicines, like ATRIPLA, for a long time.
- If you also have hepatitis B virus (HBV) infection and you stop taking ATRIPLA, you may get a "flare-up" of your hepatitis. A "flare-up" is when the disease suddenly returns in a worse way than before. Patients with HBV who stop taking ATRIPLA need close medical follow-up for several months, including medical exams and blood tests to check for hepatitis that could be getting worse. ATRIPLA is not approved for the treatment of HBV, so you must discuss your HBV therapy with your healthcare provider.

What is ATRIPLA?

ATRIPLA contains 3 medicines, SUSTIVA® (efavirenz), EMTRIVA® (emtricitabine) and VIREAD® (tenofovir disoproxil fumarate also called tenofovir DF) combined in one pill. EMTRIVA and VIREAD are HIV-1 (human immunodeficiency virus) nucleoside analog reverse transcriptase inhibitors (NRTIs) and SUSTIVA is an HIV-1 non-nucleoside analog reverse transcriptase inhibitor (NNRTI). VIREAD and EMTRIVA are the components of TRUVADA®. ATRIPLA can be used alone as a complete regimen, or in combination with other anti-HIV-1 medicines to treat people with HIV-1 infection. ATRIPLA is for adults age 18 and over. ATRIPLA has not been studied in children under age 18 or adults over age 65.

HIV infection destroys CD4^+ T cells, which are important to the immune system. The immune system helps fight infection. After a large number of T cells are destroyed, acquired immune deficiency syndrome (AIDS) develops.

ATRIPLA helps block HIV-1 reverse transcriptase, a viral chemical in your body (enzyme) that is needed for HIV-1 to multiply. ATRIPLA lowers the amount of HIV-1 in the blood (viral load). ATRIPLA may also help to increase the number of T cells (CD4^+ cells), allowing your immune system to improve. Lowering the amount of HIV-1 in the blood lowers the chance of death or infections that happen when your immune system is weak (opportunistic infections).

Does ATRIPLA cure HIV-1 or AIDS?

ATRIPLA does not cure HIV-1 infection or AIDS. The long-term effects of ATRIPLA are not known at this time. People taking ATRIPLA may still get opportunistic infections or other conditions that happen with HIV-1 infection. Opportunistic infections are infections that develop because the immune system is weak. Some of these conditions are pneumonia, herpes virus infections, and Mycobacterium avium complex (MAC) infection. It is very important that you see your healthcare provider regularly while taking ATRIPLA.

Does ATRIPLA reduce the risk of passing HIV-1 to others?

ATRIPLA has not been shown to lower your chance of passing HIV-1 to other people through sexual contact, sharing needles, or being exposed to your blood.

- Do not share needles or other injection equipment.
- Do not share personal items that can have blood or body fluids on them, like toothbrushes or razor blades.
- Do not have any kind of sex without protection. Always practice safer sex by using a latex or polyurethane condom or other barrier to reduce the chance of sexual contact with semen, vaginal secretions, or blood.

Who should not take ATRIPLA?

Together with your healthcare provider, you need to decide whether ATRIPLA is right for you.

Do not take ATRIPLA if you are allergic to ATRIPLA or any of its ingredients. The active ingredients of ATRIPLA are efavirenz, emtricitabine, and tenofovir DF. See the end of this leaflet for a complete list of ingredients.

What should I tell my healthcare provider before taking ATRIPLA?

Tell your healthcare provider if you:

- Are pregnant or planning to become pregnant (see "What should I avoid while taking ATRIPLA?").
- Are breastfeeding (see "What should I avoid while taking ATRIPLA?").
- Have kidney problems or are undergoing kidney dialysis treatment.
- Have bone problems.
- Have liver problems, including hepatitis B virus infection. Your healthcare provider may want to do tests to check your liver while you take ATRIPLA.
- Have ever had mental illness or are using drugs or alcohol.
- Have ever had seizures or are taking medicine for seizures.

What important information should I know about taking other medicines with ATRIPLA?

ATRIPLA may change the effect of other medicines, including the ones for HIV-1, and may cause serious side effects. Your healthcare provider may change your other medicines or change their doses. Other medicines, including herbal products, may affect ATRIPLA. For this reason, it is very important to let all your healthcare providers and pharmacists know what medications, herbal supplements, or vitamins you are taking.

MEDICINES YOU SHOULD NOT TAKE WITH ATRIPLA

- The following medicines may cause serious and life-threatening side effects when taken with ATRIPLA. You should not take any of these medicines while taking ATRIPLA: Vascor (bepridil), Propulsid (cisapride), Versed (midazolam), Orap (pimozide), Halcion (triazolam), ergot medications (for example, Wigraine and Cafergot).
- ATRIPLA also should not be used with Combivir (lamivudine/zidovudine), EMTRIVA, Epivir, Epivir-HBV (lamivudine), Epzicom (abacavir sulfate/lamivudine), Trizivir (abacavir sulfate/lamivudine/zidovudine), SUSTIVA, TRUVADA, or VIREAD.
- Vfend (voriconazole) should not be taken with ATRIPLA since it may lose its effect or may increase the chance of having side effects from ATRIPLA.
- Do not take St. John's wort (Hypericum perforatum), or products containing St. John's wort with ATRIPLA. St. John's wort is an herbal product sold as a dietary supplement. Talk with your healthcare provider if you are taking or are planning to take St. John's wort. Taking St. John's wort may decrease ATRIPLA levels and lead to increased viral load and possible resistance to ATRIPLA or cross-resistance to other anti-HIV-1 drugs.
- ATRIPLA should not be used with HEPSERA® (adefovir dipivoxil).

It is also important to tell your healthcare provider if you are taking any of the following:

- Fortovase, Invirase (saquinavir), Biaxin (clarithromycin); or Sporanox (itraconazole); these medicines may need to be replaced with another medicine when taken with ATRIPLA.
- Calcium channel blockers such as Cardizem or Tiazac (diltiazem), Covera HS or Isoptin (verapamil) and others; Crixivan (indinavir); the immunosuppressant medicines cyclosporine (Gengraf, Neoral, Sandimmune, and others), Prograf (tacrolimus), or Rapamune (sirolimus); Methadone; Mycobutin (rifabutin); Rifampin; cholesterol-lowering medicines such as Lipitor (atorvastatin), Pravachol (pravastatin sodium), and Zocor (simvastatin); or Zoloft (sertraline); these medicines may need to have their dose changed when taken with ATRIPLA.
- Videx, Videx EC (didanosine); tenofovir DF (a component of ATRIPLA) may increase the amount of didanosine in your blood, which could result in more side effects. You may need to be monitored more carefully if you are taking ATRIPLA and didanosine together. Also, the dose of didanosine may need to be changed.
- Reyataz (atazanavir sulfate) or Kaletra (lopinavir/ritonavir); these medicines may increase the amount of tenofovir DF (a component of ATRIPLA) in your blood, which could result in more side effects. Reyataz is not recommended with ATRIPLA. You may need to be monitored more carefully if you are taking ATRIPLA and Kaletra together. Also, the dose of Kaletra may need to be changed.
- Medicine for seizures [for example, Dilantin (phenytoin), Tegretol (carbamazepine), or phenobarbital]; your healthcare provider may want to switch you to another medicine or check drug levels in your blood from time to time.

These are not all the medicines that may cause problems if you take ATRIPLA. Be sure to tell your healthcare provider about all medicines that you take.

Keep a complete list of all the prescription and nonprescription medicines as well as any herbal remedies that you are taking, how much you take, and how often you take them. Make a new list when medicines or herbal remedies are added or stopped, or if the dose changes. Give copies of this list to all of your healthcare providers and pharmacists every time you visit your healthcare provider or fill a prescription. This will give your healthcare provider a complete picture of the medicines you use. Then he or she can decide the best approach for your situation.

How should I take ATRIPLA?

- Take the exact amount of ATRIPLA your healthcare provider prescribes. Never change the dose on your own. Do not stop this medicine unless your healthcare provider tells you to stop.
- You should take ATRIPLA on an empty stomach.
- Swallow ATRIPLA with water.
- Taking ATRIPLA at bedtime may make some side effects less bothersome.
- Do not miss a dose of ATRIPLA. If you forget to take ATRIPLA, take the missed dose right away, unless it is almost time for your next dose. Do not double the next dose. Carry on with your regular dosing schedule. If you need help in planning the best times to take your medicine, ask your healthcare provider or pharmacist.
- If you believe you took more than the prescribed amount of ATRIPLA, contact your local poison control center or emergency room right away.
- Tell your healthcare provider if you start any new medicine or change how you take old ones. Your doses may need adjustment.
- When your ATRIPLA supply starts to run low, get more from your healthcare provider or pharmacy. This is very important because the amount of virus in your blood may increase if the medicine is stopped for even a short time. The virus may develop resistance to ATRIPLA and become harder to treat.
- Your healthcare provider may want to do blood tests to check for certain side effects while you take ATRIPLA.

What should I avoid while taking ATRIPLA?

- Women should not become pregnant while taking ATRIPLA and for 12 weeks after stopping it. Serious birth defects have been seen in the babies of animals and women treated with efavirenz (a component of ATRIPLA) during pregnancy. It is not known whether efavirenz caused these defects. Tell your healthcare provider right away if you are pregnant. Also talk with your healthcare provider if you want to become pregnant.
- Women should not rely only on hormone-based birth control, such as pills, injections, or implants, because ATRIPLA may make these contraceptives ineffective. Women must use a reliable form of barrier contraception, such as a condom or diaphragm, even if they also use other methods of birth control. Efavirenz, a component of ATRIPLA, may remain in your blood for a time after therapy is stopped. Therefore, you should continue to use contraceptive measures for 12 weeks after you stop taking ATRIPLA.
- Do not breast-feed if you are taking ATRIPLA. The Centers for Disease Control and Prevention recommend that mothers with HIV not breast-feed because they can pass the HIV through their milk to the baby. Also, ATRIPLA may pass through breast milk and cause serious harm to the baby. Talk with your healthcare provider if you are breast-feeding. You should stop breast-feeding or may need to use a different medicine.
- Taking ATRIPLA with alcohol or other medicines causing similar side effects as ATRIPLA, such as drowsiness, may increase those side effects.
- Do not take any other medicines, including prescription and nonprescription medicines and herbal products, without checking with your healthcare provider.
- Avoid doing things that can spread HIV-1 infection since ATRIPLA does not stop you from passing the HIV-1 infection to others.

What are the possible side effects of ATRIPLA?

ATRIPLA may cause the following serious side effects:

- Lactic acidosis (buildup of an acid in the blood). Lactic acidosis can be a medical emergency and may need to be treated in the hospital. Call your healthcare provider right away if you get signs of lactic acidosis. (See "What is the most important information I should know about ATRIPLA?")
- Serious liver problems (hepatotoxicity), with liver enlargement (hepatomegaly) and fat in the liver (steatosis). Call your healthcare provider right away if you get any signs of liver problems. (See "What is the most important information I should know about ATRIPLA?")
- "Flare-ups" of hepatitis B virus (HBV) infection, in which the disease suddenly returns in a worse way than before, can occur if you have HBV and you stop taking ATRIPLA. Your healthcare provider will monitor your condition for several months after stopping ATRIPLA if you have both HIV-1 and HBV infection and may recommend treatment for your HBV. ATRIPLA is not approved for the treatment of hepatitis B virus infection. If you have advanced liver disease and stop treatment with ATRIPLA, the "flare-up" of hepatitis B may cause your liver function to decline.
- Serious psychiatric problems. A small number of patients may experience severe depression, strange thoughts, or angry behavior while taking ATRIPLA. Some patients have thoughts of suicide and a few have actually committed suicide. These problems may occur more often in patients who have had mental illness. Contact your healthcare provider right away if you think you are having these psychiatric symptoms, so your healthcare provider can decide if you should continue to take ATRIPLA.
- Kidney problems (including decline or failure of kidney function). If you have had kidney problems in the past or take other medicines that can cause kidney problems, your healthcare provider should do regular blood tests to check your kidneys. Symptoms that may be related to kidney problems include a high volume of urine, thirst, muscle pain, and muscle weakness.
- Changes in bone mineral density (thinning bones). Laboratory tests show changes in the bones of patients treated with tenofovir DF, a component of ATRIPLA. Some HIV patients treated with tenofovir DF developed thinning of the bones (osteopenia) which could lead to fractures. If you have had bone problems in the past, your healthcare provider may need to do tests to check your bone mineral density or may prescribe medicines to help your bone mineral density. Additionally, bone pain and softening of the bone (which may contribute to fractures) may occur as a consequence of kidney problems.

Common side effects:

Patients may have dizziness, headache, trouble sleeping, drowsiness, trouble concentrating, and/or unusual dreams during treatment with ATRIPLA. These side effects may be reduced if you take ATRIPLA at bedtime on an empty stomach. They also tend to go away after you have taken the medicine for a few weeks. If you have these common side effects, such as dizziness, it does not mean that you will also have serious psychiatric problems, such as severe depression, strange thoughts, or angry behavior. Tell your healthcare provider right away if any of these side effects continue or if they bother you. It is possible that these symptoms may be more severe if ATRIPLA is used with alcohol or mood altering (street) drugs.

If you are dizzy, have trouble concentrating, or are drowsy, avoid activities that may be dangerous, such as driving or operating machinery.

Rash may be common. Rashes usually go away without any change in treatment. In a small number of patients, rash may be serious. If you develop a rash, call your healthcare provider right away.

Other common side effects include tiredness, upset stomach, vomiting, gas, and diarrhea.

Other possible side effects with ATRIPLA:

- Changes in body fat. Changes in body fat develop in some patients taking anti HIV-1 medicine. These changes may include an increased amount of fat in the upper back and neck ("buffalo hump"), in the breasts, and around the trunk. Loss of fat from the legs, arms, and face may also happen. The cause and long-term health effects of these fat changes are not known.
- Skin discoloration (small spots or freckles) may also happen with ATRIPLA.
- In some patients with advanced HIV infection (AIDS), signs and symptoms of inflammation from previous infections may occur soon after anti-HIV treatment is started. It is believed that these symptoms are due to an improvement in the body's immune response, enabling the body to fight infections that may have been present with no obvious symptoms. If you notice any symptoms of infection, please inform your doctor immediately.
- Additional side effects are inflammation of the pancreas, allergic reaction (including swelling of the face, lips, tongue, or throat), shortness of breath, pain, stomach pain, weakness and indigestion.

Tell your healthcare provider or pharmacist if you notice any side effects while taking ATRIPLA.

Contact your healthcare provider before stopping ATRIPLA because of side effects or for any other reason.

This is not a complete list of side effects possible with ATRIPLA. Ask your healthcare provider or pharmacist for a more complete list of side effects of ATRIPLA and all the medicines you will take.

How do I store ATRIPLA?

- Keep ATRIPLA and all other medicines out of reach of children.
- Store ATRIPLA at room temperature 77 °F (25 °C).
- Keep ATRIPLA in its original container and keep the container tightly closed.
- Do not keep medicine that is out of date or that you no longer need. If you throw any medicines away make sure that children will not find them.

General information about ATRIPLA:

Medicines are sometimes prescribed for conditions that are not mentioned in patient information leaflets. Do not use ATRIPLA for a condition for which it was not prescribed. Do not give ATRIPLA to other people, even if they have the same symptoms you have. It may harm them.

This leaflet summarizes the most important information about ATRIPLA. If you would like more information, talk with your healthcare provider. You can ask your healthcare provider or pharmacist for information about ATRIPLA that is written for health professionals.

Do not use ATRIPLA if the seal over bottle opening is broken or missing.

What are the ingredients of ATRIPLA?

Active Ingredients: efavirenz, emtricitabine, and tenofovir disoproxil fumarate

Inactive Ingredients: croscarmellose sodium, hydroxypropyl cellulose, microcrystalline cellulose, magnesium stearate, sodium lauryl sulfate. The film coating contains black iron oxide, polyethylene glycol, polyvinyl alcohol, red iron oxide, talc, and titanium dioxide.

Rx Only

ATRIPLA is a trademark of Bristol-Myers Squibb & Gilead Sciences, LLC. EMTRIVA, TRUVADA, HEPSERA and VIREAD are trademarks of Gilead Sciences, Inc. SUSTIVA is a trademark of Bristol-Myers Squibb Pharma Company. Reyataz and Videx are trademarks of Bristol-Myers Squibb Company. Pravachol is a trademark of ER Squibb & Sons, LLC. Other brands listed are the trademarks of their respective owners.

This product was Repackaged By:

State of Florida DOH Central Pharmacy
104-2 Hamilton Park Drive
Tallahassee, FL 32304
United States

PACKAGE LABEL

PRINCIPAL DISPLAY PANEL - 30 Tablet Blister Pack

NDC 53808-0208-1

ATRIPLA®

(efavirenz 600 mg/emtricitabine 200 mg/
tenofovir disoproxil fumarate 300 mg)
Tablets

30 tablets

Note to pharmacist: Do not cover ALERT box with pharmacy label.

ALERT: Find out about medicines that
should NOT be taken with ATRIPLA®